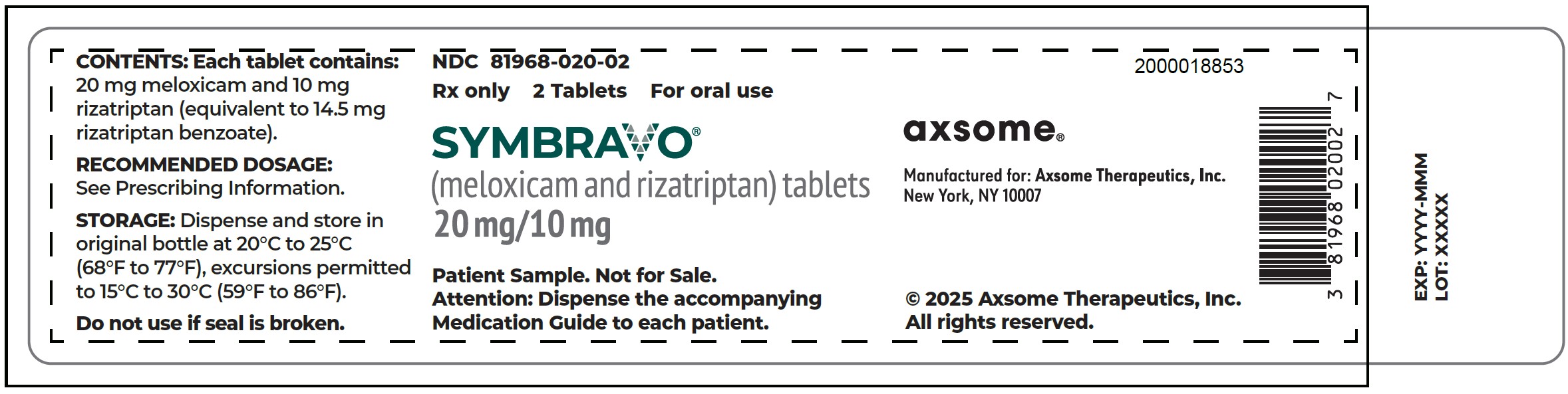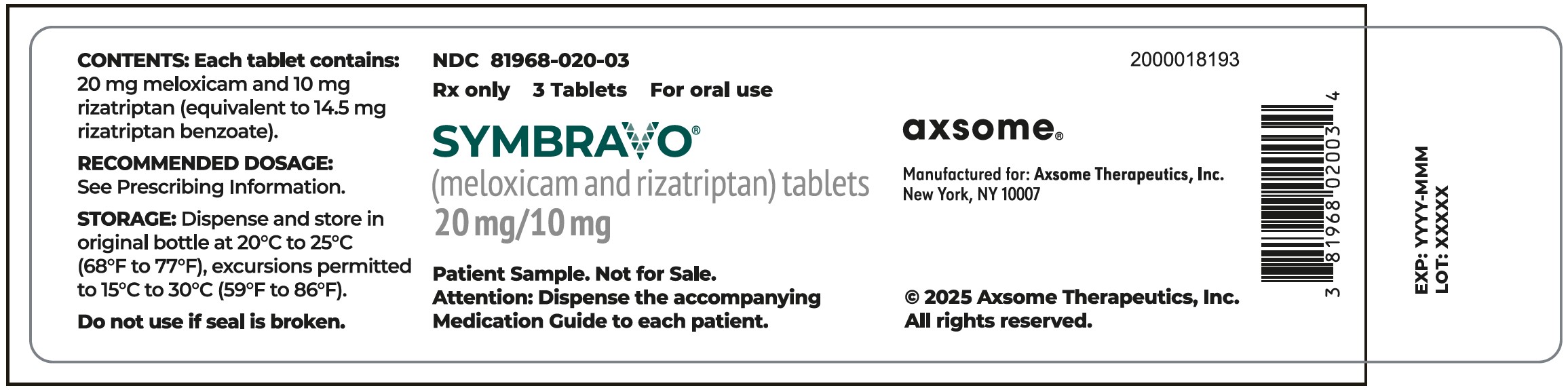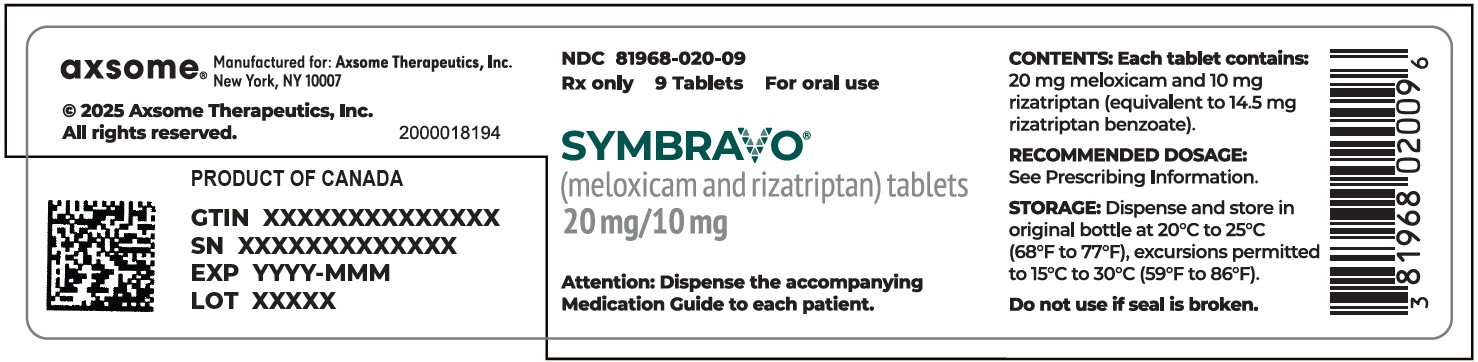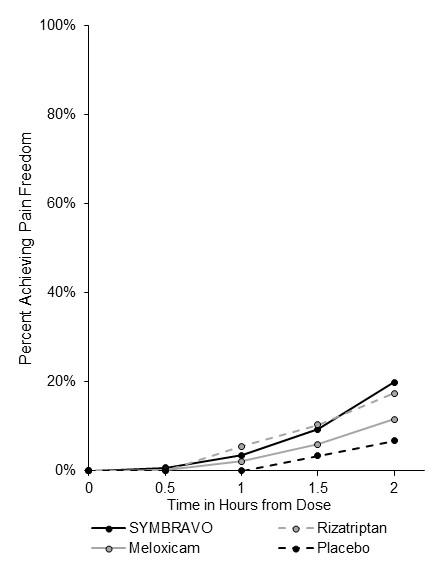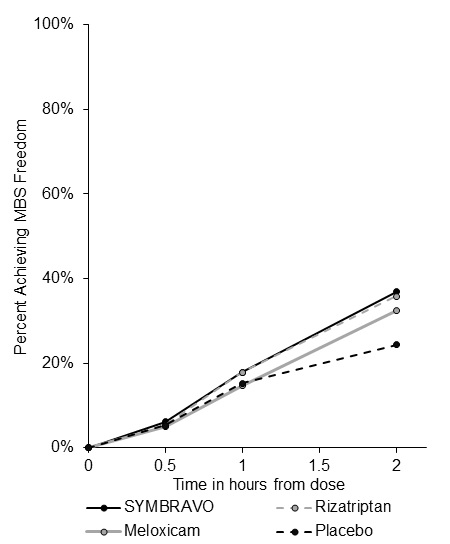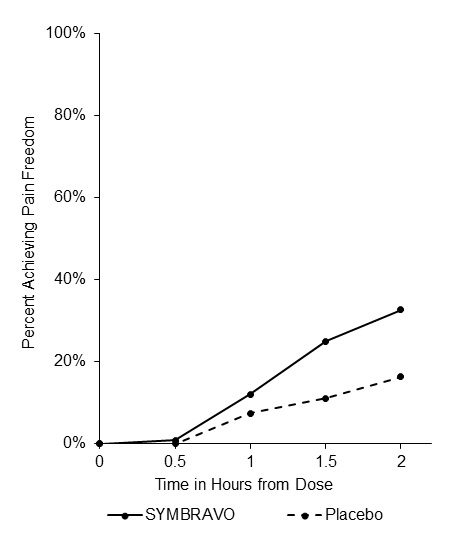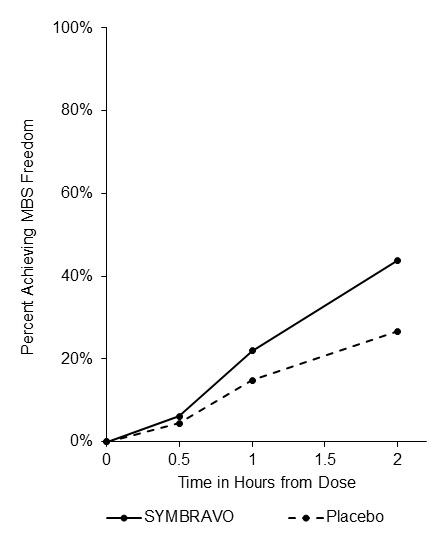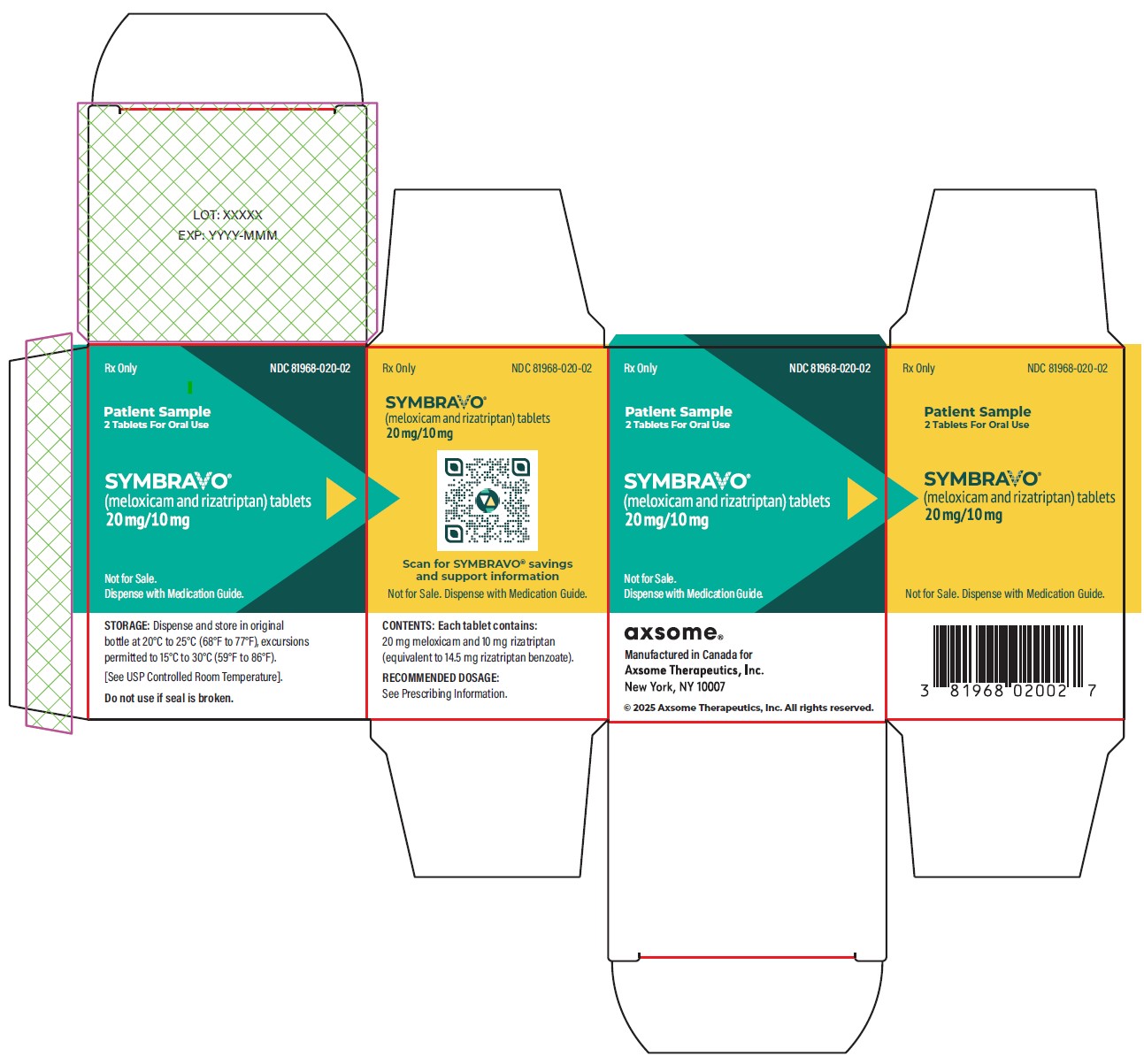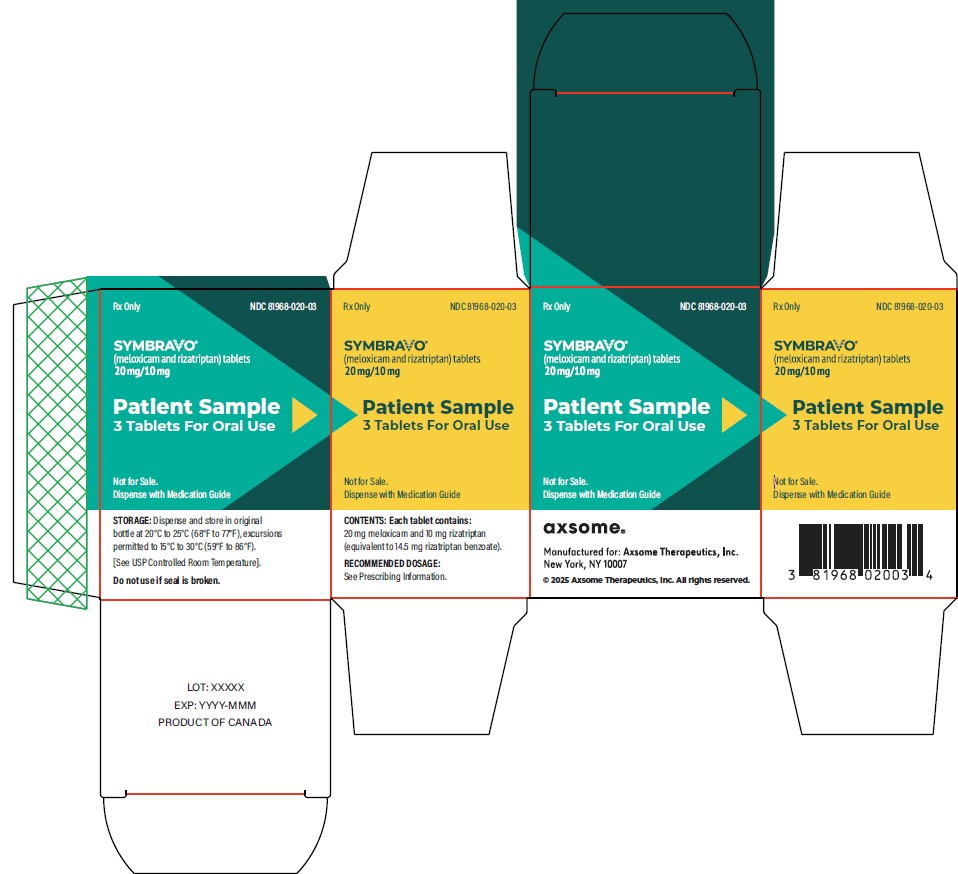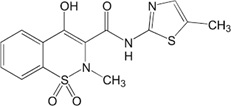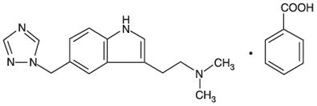 DRUG LABEL: SYMBRAVO
NDC: 81968-020 | Form: TABLET
Manufacturer: Axsome Therapeutics, Inc.
Category: prescription | Type: HUMAN PRESCRIPTION DRUG LABEL
Date: 20251121

ACTIVE INGREDIENTS: MELOXICAM 20 mg/1 1; RIZATRIPTAN BENZOATE 10 mg/1 1
INACTIVE INGREDIENTS: BETADEX SULFOBUTYL ETHER SODIUM; STARCH, CORN; SILICON DIOXIDE; POVIDONE; CROSPOVIDONE; MAGNESIUM STEARATE; TALC; TITANIUM DIOXIDE; SODIUM BICARBONATE; MICROCRYSTALLINE CELLULOSE; POLYVINYL ALCOHOL, UNSPECIFIED; POLYETHYLENE GLYCOL, UNSPECIFIED

HIGHLIGHTS OF PRESCRIBING INFORMATION

These highlights do not include all the information needed to use SYMBRAVO safely and effectively. See full prescribing information for SYMBRAVO.
SYMBRAVO (meloxicam and rizatriptan) tablets, for oral use
Initial U.S. Approval: 2025

WARNING: RISK OF SERIOUS CARDIOVASCULAR AND GASTROINTESTINAL EVENTS

See full prescribing information for complete boxed warning.

- Non-steroidal anti-inflammatory drugs (NSAIDs) cause an increased risk of serious cardiovascular thrombotic events, including myocardial infarction, and stroke, which can be fatal. This risk may occur early in treatment and may increase with duration of use (5.1).
- SYMBRAVO is contraindicated in the setting of coronary artery bypass graft (CABG) surgery (4, 5.1).
- NSAIDs cause an increased risk of serious gastrointestinal (GI) adverse events including bleeding, ulceration, and perforation of the stomach or intestines, which can be fatal. These events can occur at any time during use and without warning symptoms. Elderly patients and patients with a prior history of peptic ulcer disease and/or GI bleeding are at greater risk for serious GI events (5.2).

1 INDICATIONS AND USAGE

SYMBRAVO is a combination of meloxicam (an NSAID) and rizatriptan (a serotonin (5-HT) 1B/1D receptor agonist (triptan)), indicated for the acute treatment of migraine with or without aura in adults (1).

Limitations of Use

- SYMBRAVO should only be used where a clear diagnosis of migraine has been established (1).
- SYMBRAVO is not indicated for the preventive treatment of migraine (1).
- SYMBRAVO is not indicated for the treatment of cluster headache (1).

2 DOSAGE AND ADMINISTRATION

- The recommended dose of SYMBRAVO is one tablet by mouth as needed (2.1).
- The maximum daily dose is 20 mg meloxicam and 10 mg rizatriptan (1 tablet) (2.1).

3 DOSAGE FORMS AND STRENGTHS

Tablets: 20 mg meloxicam and 10 mg rizatriptan (3)

4 CONTRAINDICATIONS

- Ischemic coronary artery disease or other significant underlying cardiovascular disease (4)
- Coronary artery vasospasm (4)
- In the setting of CABG surgery (4)
- History of stroke or transient ischemic attack (4)
- Hemiplegic or basilar migraine (4)
- Peripheral vascular disease (4)
- Ischemic bowel disease (4)
- Uncontrolled hypertension (4)
- Concomitant use of propranolol (4)
- Recent (within 24 hours) use of an ergotamine-containing medication, ergot-type medication (such as dihydroergotamine or methysergide), another 5-HT1 agonist (e.g., another triptan) (4)
- Concurrent administration or recent discontinuation (i.e., within the past 2 weeks) of a MAO-A inhibitor (4)
- Known hypersensitivity to SYMBRAVO, meloxicam, rizatriptan, NSAIDs, triptans, or any of the excipients in SYMBRAVO (4)
- History of asthma, urticaria, or other allergic-type reactions after taking aspirin or other NSAIDs (4)
- Moderate to severe renal insufficiency in patients who are at risk for renal failure due to volume depletion or who are on dialysis (4)

5 WARNINGS AND PRECAUTIONS

- Cardiovascular Thrombotic Events, Myocardial Ischemia, Myocardial Infarction, and Prinzmetal's Angina: Perform cardiac evaluation in patients with multiple cardiovascular risk factors (5.1).
- Arrhythmias: Discontinue dosing if arrhythmia occurs (5.3).
- Cerebral Hemorrhage, Subarachnoid Hemorrhage, and Stroke: Discontinue dosing if occurs (5.4).
- Anaphylactic Reactions: Seek emergency help if an anaphylactic reaction occurs (5.5).
- Chest/Throat/Neck/Jaw Pain, Tightness, Pressure, or Heaviness: Generally not associated with myocardial ischemia; evaluate patients at high risk (5.6).
- Gastrointestinal Ischemic Events, Peripheral Vasospastic Reactions: Discontinue dosing if occurs (5.7).
- Hepatotoxicity: Inform patients of warning signs and symptoms of hepatotoxicity. Discontinue if abnormal liver tests persist or worsen or if clinical signs and symptoms of liver disease develop (5.8).
- Hypertension: Patients taking some antihypertensive medications may have impaired response to these therapies when taking NSAIDs. Monitor blood pressure (5.9, 7.1).
- Heart Failure and Edema: Avoid use of SYMBRAVO in patients with severe heart failure unless benefits are expected to outweigh risk of worsening heart failure (5.10).
- Renal Toxicity and Hyperkalemia: Monitor renal function in patients with renal or hepatic impairment, heart failure, dehydration, or hypovolemia. Use is not recommended in patients with moderate to severe renal insufficiency; avoid the use in patients with advanced renal disease unless the benefits are expected to outweigh the risk of worsening renal function (4, 5.11).
- Serious Skin Reactions: Discontinue SYMBRAVO at first appearance of skin rash or other signs of hypersensitivity (5.12).
- Drug Reaction with Eosinophilia and Systemic Symptoms (DRESS): Discontinue SYMBRAVO and evaluate clinically (5.13).
- Fetal Toxicity: Limit use of NSAIDs, including SYMBRAVO, between about 20 to 30 weeks in pregnancy due to the risk of oligohydramnios/fetal renal dysfunction. Avoid use of NSAIDs in women at about 30 weeks gestation and later in pregnancy due to the risks of oligohydramnios/fetal renal dysfunction and premature closure of the fetal ductus arteriosus (5.14, 8.1).
- Hematologic Toxicity: Monitor hemoglobin or hematocrit in patients with any signs or symptoms of anemia (5.15, 7.1).
- Exacerbation of Asthma Related to Aspirin Sensitivity: SYMBRAVO is contraindicated in patients with aspirin-sensitive asthma. Monitor patients with preexisting asthma (without aspirin sensitivity) (5.16).
- Medication Overuse Headache: Detoxification may be necessary (5.17).
- Serotonin Syndrome: Discontinue dosing if occurs (5.18).

6 ADVERSE REACTIONS

Most common adverse reactions (≥1% and greater than placebo) are dizziness and somnolence (6.1).

To report SUSPECTED ADVERSE REACTIONS, contact Axsome Therapeutics at 1-800-484-1672 or FDA at 1-800-FDA-1088 or www.fda.gov/medwatch.

7 DRUG INTERACTIONS

- Drugs that Interfere with Hemostasis (e.g., warfarin, aspirin, SSRIs/SNRIs): Monitor patients for bleeding who are concomitantly taking SYMBRAVO with drugs that interfere with hemostasis. Concomitant use of SYMBRAVO and analgesic doses of aspirin is not generally recommended (7.1).
- ACE Inhibitors, ARBs, or Beta-Blockers: Concomitant use with SYMBRAVO may diminish the antihypertensive effect of these drugs. Monitor blood pressure (7.1).
- ACE Inhibitors and ARBs: Concomitant use with SYMBRAVO in elderly, volume-depleted, or those with renal impairment may result in deterioration of renal function. In such high-risk patients, monitor for signs of worsening renal function (7.1).
- Diuretics: NSAIDs can reduce natriuretic effect of furosemide and thiazide diuretics. Monitor patients to assure diuretic efficacy including antihypertensive effects (7.1).
- Lithium: Monitor for increases in lithium plasma levels (7.1)
- Methotrexate: Monitor for increases methotrexate plasma levels. (7.1).

8 USE IN SPECIFIC POPULATIONS

- Infertility: NSAIDs are associated with reversible infertility. Consider withdrawal of SYMBRAVO in women who have difficulties conceiving (8.3).

FULL PRESCRIBING INFORMATION

WARNING: RISK OF SERIOUS CARDIOVASCULAR AND GASTROINTESTINAL EVENTS

Cardiovascular Risk

- Non-steroidal anti-inflammatory drugs (NSAIDs) cause an increased risk of serious cardiovascular thrombotic events, including myocardial infarction and stroke, which can be fatal. This risk may occur early in treatment and may increase with duration of use [see Warnings & Precautions (5.1)].
- SYMBRAVO is contraindicated in the setting of coronary artery bypass graft (CABG) surgery [see Contraindications (4), Warnings & Precautions (5.1)].

Gastrointestinal Risk

- NSAIDs cause an increased risk of serious gastrointestinal (GI) adverse events including bleeding, ulceration, and perforation of the stomach or intestines, which can be fatal. These events can occur at any time during use and without warning symptoms. Elderly patients and patients with a prior history of peptic ulcer disease and/or GI bleeding are at greater risk for serious GI events [see Warnings & Precautions (5.2)].

1 INDICATIONS AND USAGE

SYMBRAVO is indicated for the acute treatment of migraine with or without aura in adults.

Limitations of Use

- SYMBRAVO should only be used where a clear diagnosis of migraine has been established. If a patient has no response for the first migraine attack treated with SYMBRAVO, the diagnosis of migraine should be reconsidered before SYMBRAVO is administered to treat any subsequent attacks.
- SYMBRAVO is not indicated for the preventive treatment of migraine attacks.
- SYMBRAVO is not indicated for the treatment of cluster headache.

2 DOSAGE AND ADMINISTRATION

2.1 Recommended Dose

The recommended dose of SYMBRAVO is one tablet (containing 20 mg meloxicam and 10 mg rizatriptan) by mouth, as needed for the acute treatment of migraine. The maximum daily dose should not exceed one tablet. The safety and effectiveness of a second dose for the same migraine attack have not been established. The safety of treating, on average, more than 7 headaches in a 30-day period has not been established.

Use for the shortest duration consistent with individual patient treatment goals [see Warnings and Precautions (5)].

2.2 Administration

Swallow SYMBRAVO tablets whole. Do not crush, divide, or chew the tablets. SYMBRAVO can be taken with or without food.

2.3 Not Substitutable with Other Formulations of Meloxicam and of Rizatriptan

SYMBRAVO tablets have not shown equivalent systemic exposures to other formulations of oral meloxicam and of oral rizatriptan. Therefore, SYMBRAVO tablets are not substitutable with other formulations of oral meloxicam or oral rizatriptan products, even if the milligram strengths are the same. Do not substitute SYMBRAVO with similar dose strengths of other meloxicam or rizatriptan products [see Clinical Pharmacology (12.3)].

3 DOSAGE FORMS AND STRENGTHS

Tablets: 20 mg meloxicam and 10 mg rizatriptan, white and modified capsule-shaped, debossed with “MXRZ” on one side and “20/10” on the other.

4 CONTRAINDICATIONS

SYMBRAVO is contraindicated in patients with:

- Ischemic coronary artery disease (angina pectoris, history of myocardial infarction, or documented silent ischemia), or other significant underlying cardiovascular disease [see Warnings & Precautions (5.1)].
- Coronary artery vasospasm including Prinzmetal’s angina [see Warnings & Precautions (5.1)].
- In the setting of coronary artery bypass graft (CABG) surgery [see Warnings & Precautions (5.1)].
- History of stroke or transient ischemic attack (TIA) [see Warnings & Precautions (5.4)].
- Hemiplegic or basilar migraine.
- Peripheral vascular disease (PVD) [see Warnings & Precautions (5.7)].
- Ischemic bowel disease [see Warnings & Precautions (5.7)].
- Uncontrolled hypertension [see Warnings & Precautions (5.9)].
- Concomitant use of propranolol [see Drug Interactions (7.1)]
- Recent use (i.e., within 24 hours) of an ergotamine-containing medication, ergot-type medication (such as dihydroergotamine or methysergide), or another 5-HT1 agonist (e.g., another triptan) [see Drug Interactions (7.1)].
- Concurrent administration or recent discontinuation (i.e., within 2 weeks) of a MAO-A inhibitor [see Drug Interactions (7.1), Clinical Pharmacology (12.3)].
- Known hypersensitivity (e.g., anaphylactic reactions and angioedema seen) to SYMBRAVO, meloxicam, rizatriptan, NSAIDs or any of the excipients in SYMBRAVO [see Warnings & Precautions (5.5), Adverse Reactions (6.2)].
- History of asthma, urticaria, or other allergic-type reactions after taking aspirin or other NSAIDs. Severe, sometimes fatal anaphylactic-like reactions to NSAIDs have been reported in such patients [see Warnings & Precautions (5.16)].
- Moderate to severe renal insufficiency in patients who are at risk for renal failure due to volume depletion or who are on dialysis [see Warnings & Precautions (5.11)].

5 WARNINGS AND PRECAUTIONS

5.1 Cardiovascular Thrombotic Events and Myocardial Infarction

Cardiovascular Thrombotic Events with NSAIDS

Clinical trials of several COX-2 selective and nonselective NSAIDs of up to three years duration have shown an increased risk of serious cardiovascular (CV) thrombotic events, including myocardial infarction (MI) and stroke, which can be fatal. Based on available data, it is unclear that the risk for CV thrombotic events is similar for all NSAIDs. The relative increase in serious CV thrombotic events over baseline conferred by NSAID use appears to be similar in those with and without known CV disease or risk factors for CV disease. However, patients with known CV disease or risk factors had a higher absolute incidence of excess serious CV thrombotic events, due to their increased baseline rate. Some observational studies found that this increased risk of serious CV thrombotic events began as early as the first weeks of treatment. The increase in CV thrombotic risk has been observed most consistently at higher doses.

To minimize the potential risk for an adverse CV event in NSAID-treated patients, use the lowest effective dose for the shortest duration possible. Physicians and patients should remain alert for the development of such events, throughout the entire treatment course, even in the absence of previous CV symptoms. Patients should be informed about the symptoms of serious CV events and the steps to take if they occur.

There is no consistent evidence that concurrent use of aspirin mitigates the increased risk of serious CV thrombotic events associated with NSAID use. The concurrent use of aspirin and an NSAID, such as meloxicam, increases the risk of serious gastrointestinal (GI) events [see Warnings & Precautions (5.2)].

Status Post Coronary Artery Bypass Graft (CABG) Surgery

Two large, controlled clinical trials of a COX-2 selective NSAID for the treatment of pain in the first 10-14 days following CABG surgery found an increased incidence of MI and stroke. NSAIDs are contraindicated in the setting of CABG [see Contraindications (4)].

Post-MI Patients

Observational studies conducted in the Danish National Registry have demonstrated that patients treated with NSAIDs in the post-MI period were at increased risk of reinfarction, CV-related death, and all-cause mortality beginning in the first week of treatment. In this same cohort, the incidence of death in the first year post-MI was 20 per 100 person years in NSAID-treated patients compared to 12 per 100 person years in non-NSAID exposed patients. Although the absolute rate of death declined somewhat after the first year post-MI, the increased relative risk of death in NSAID users persisted over at least the next four years of follow-up.

Myocardial Ischemia, Myocardial Infarction, and Prinzmetal’s Angina with Rizatriptan

SYMBRAVO should not be given to patients with ischemic or vasospastic coronary artery disease. There have been rare reports of serious cardiac adverse reactions, including acute myocardial infarction, occurring within a few hours following administration of rizatriptan. Some of these reactions occurred in patients without known coronary artery disease (CAD). 5-HT1 agonists, including SYMBRAVO may cause coronary artery vasospasm (Prinzmetal’s Angina), even in patients without a history of CAD [see Contraindications (4)].

Triptan-naïve patients who have multiple cardiovascular risk factors (e.g., increased age, diabetes, hypertension, smoking, obesity, strong family history of CAD) should have a cardiovascular evaluation prior to receiving SYMBRAVO. If there is evidence of CAD or coronary artery vasospasm, SYMBRAVO should not be administered [see Contraindications (4)]. For patients who have a negative cardiovascular evaluation, consideration should be given to administration of the first dose of SYMBRAVO in a medically-supervised setting and performing an electrocardiogram (ECG) immediately following SYMBRAVO administration. Periodic cardiovascular evaluation should be considered in intermittent long-term users of SYMBRAVO who have cardiovascular risk factors.

Avoid the use of SYMBRAVO in patients with a recent MI unless the benefits are expected to outweigh the risk of recurrent CV thrombotic events. If SYMBRAVO is used in patients with a recent MI, monitor patients for signs of cardiac ischemia.

5.2 Gastrointestinal Bleeding, Ulceration, and Perforation

NSAIDs, including meloxicam, a component of SYMBRAVO, can cause serious GI adverse events including inflammation, bleeding, ulceration, and perforation of the esophagus, stomach, small intestine, or large intestine, which can be fatal. These serious adverse events can occur at any time, with or without warning symptoms, in patients treated with meloxicam. Only 1 in 5 patients who develop a serious upper GI adverse event on NSAID therapy is symptomatic. Upper GI ulcers, gross bleeding, or perforation caused by NSAIDs occurred in approximately 1% of patients treated for 3-6 months, and in about 2-4% of patients treated for one year. However, even short-term NSAID therapy is not without risk.

Risk Factors for GI Bleeding, Ulceration, and Perforation

Patients with a prior history of peptic ulcer disease and/or GI bleeding who used NSAIDs had a greater than 10-fold increased risk for developing a GI bleed compared to patients without these risk factors. Other factors that increase the risk of GI bleeding in patients treated with NSAIDs include longer duration of NSAID therapy; concomitant use of oral corticosteroids, aspirin, anticoagulants, or selective SSRIs; smoking; use of alcohol; older age; and poor general health status. Most postmarketing reports of fatal GI events occurred in elderly or debilitated patients. Additionally, patients with advanced liver disease and/or coagulopathy are at increased risk for GI bleeding.

Strategies to Minimize the GI Risks in NSAID-Treated Patients:

- Use the lowest effective dosage for the shortest possible duration.
- Avoid administration of more than one NSAID at a time.
- Avoid use in patients at higher risk unless benefits are expected to outweigh the increased risk of bleeding. For such patients, as well as those with active GI bleeding, consider alternate therapies other than NSAIDs.
- Remain alert for signs and symptoms of GI ulceration and bleeding during NSAID therapy.
- If a serious GI adverse event is suspected, promptly initiate evaluation and treatment, and discontinue SYMBRAVO until a serious GI adverse event is ruled out.
- In the setting of concomitant use of low-dose aspirin for cardiac prophylaxis, monitor patients more closely for evidence of GI bleeding [see Drug Interactions (7.1)].

5.3 Arrhythmias

Life-threatening disturbances of cardiac rhythm, including ventricular tachycardia and ventricular fibrillation leading to death, have been reported within a few hours following the administration of 5-HT1 agonists. Discontinue SYMBRAVO if these disturbances occur.

5.4 Cerebrovascular Events

Cerebral hemorrhage, subarachnoid hemorrhage, and stroke have occurred in patients treated with 5-HT1 agonists, and some have resulted in fatalities. In a number of cases, it appears possible that the cerebrovascular events were primary, the 5-HT1 agonist having been administered in the incorrect belief that the symptoms experienced were a consequence of migraine, when they were not. Also, patients with migraine may be at increased risk of certain cerebrovascular events (e.g., stroke, hemorrhage, transient ischemic attack). Discontinue SYMBRAVO if a cerebrovascular event occurs.

Before treating headaches in patients not previously diagnosed with migraine, and in patients with migraine who present with atypical symptoms, care should be taken to exclude other potentially serious neurological conditions. SYMBRAVO is contraindicated in patients with a history of stroke or transient ischemic attack [see Contraindications (4)].

5.5 Anaphylactic Reactions

SYMBRAVO can cause anaphylactic reactions. Meloxicam has been associated with anaphylactic reactions in patients with and without known hypersensitivity to meloxicam and in patients with aspirin-sensitive asthma. Hypersensitivity reactions, including angioedema and anaphylaxis, have also occurred in patients receiving rizatriptan. Seek emergency help if an anaphylactic reaction occurs [see Contraindications (4), Warnings and Precautions (5.16)].

5.6 Chest, Throat, Neck and/or Jaw Pain/Tightness/Pressure

Sensations of tightness, pain, pressure, and heaviness in the precordium, throat, neck and jaw commonly occur after treatment with SYMBRAVO and are usually non-cardiac in origin. However, if a cardiac origin is suspected, patients should be evaluated. SYMBRAVO is contraindicated in patients with ischemic coronary artery disease and those with Prinzmetal’s variant angina [see Contraindications (4)].

5.7 Other Vasospasm Reactions

5-HT1 agonists, including SYMBRAVO, may cause non-coronary vasospastic reactions, such as peripheral vascular ischemia, gastrointestinal vascular ischemia and infarction (presenting with abdominal pain and bloody diarrhea), splenic infarction, and Raynaud’s syndrome. In patients who experience symptoms or signs suggestive of non-coronary vasospasm reaction following the use of any 5-HT1 agonist, the suspected vasospasm reaction should be ruled out before receiving additional SYMBRAVO doses.

Reports of transient and permanent blindness and significant partial vision loss have been reported with the use of 5-HT1 agonists. Since visual disorders may be part of a migraine attack, a causal relationship between these events and the use of 5-HT1 agonists has not been clearly established.

5.8 Hepatotoxicity

Elevations of ALT or AST (3- or more times the upper limit of normal [ULN]) have been reported in approximately 1% of NSAID-treated patients in clinical trials. In addition, rare, sometimes fatal, cases of severe hepatic injury, including fulminant hepatitis, liver necrosis, and hepatic failure have been reported.

Elevations of ALT or AST (less than 3-times ULN) may occur in up to 15% of patients treated with NSAIDs including meloxicam, a component of SYMBRAVO.

Inform patients of the warning signs and symptoms of hepatotoxicity (e.g., nausea, fatigue, lethargy, diarrhea, pruritus, jaundice, right upper quadrant tenderness, and "flu-like" symptoms). If clinical signs and symptoms consistent with liver disease develop, or if systemic manifestations occur (e.g., eosinophilia, rash, etc.), discontinue SYMBRAVO immediately, and perform a clinical evaluation of the patient [see Use in Specific Populations (8.7), Clinical Pharmacology (12.3)].

5.9 Hypertension/Increase in Blood Pressure

NSAIDs, including meloxicam, a component of SYMBRAVO, can lead to new onset of hypertension or worsening of pre-existing hypertension, either of which may contribute to the increased incidence of CV events. Patients taking angiotensin converting enzyme (ACE) inhibitors, thiazides or loop diuretics may have impaired response to these therapies when taking NSAIDs [see Drug Interactions (7.1)].

Significant elevation in blood pressure (BP), including hypertensive crisis with acute impairment of organ systems, has been reported on rare occasions in patients with and without a history of hypertension receiving 5-HT1 agonists, including rizatriptan, a component of SYMBRAVO. In healthy young adult male and female patients who received maximal doses of rizatriptan (10 mg every 2 hours for 3 doses), slight increases in BP (approximately 2-3 mmHg) were observed. SYMBRAVO is contraindicated in patients with uncontrolled hypertension [see Contraindications (4)].

Monitor BP during the initiation of SYMBRAVO treatment and throughout the course of therapy.

5.10 Heart Failure and Edema

The Coxib and traditional NSAID Trialists’ Collaboration meta-analysis of randomized controlled trials demonstrated an approximately 2-fold increase in hospitalizations for heart failure in COX-2 selective-treated patients and nonselective NSAID-treated patients compared to placebo-treated patients. In a Danish National Registry study of patients with heart failure, NSAID use increased the risk of MI, hospitalization for heart failure, and death.

Additionally, fluid retention and edema have been observed in some patients treated with NSAIDs. Use of SYMBRAVO may blunt the CV effects of several therapeutic agents used to treat these medical conditions (e.g., diuretics, ACE inhibitors, or angiotensin receptor blockers [ARBs]) [see Drug Interactions (7.1)].

Avoid the use of SYMBRAVO in patients with severe heart failure unless the benefits are expected to outweigh the risk of worsening heart failure. If SYMBRAVO is used in patients with severe heart failure, monitor patients for signs of worsening heart failure.

5.11 Renal Toxicity and Hyperkalemia

Renal Toxicity

Long-term administration of NSAIDs has resulted in renal papillary necrosis, renal insufficiency, acute renal failure, and other renal injury.

Renal toxicity has also been seen in patients in whom renal prostaglandins have a compensatory role in the maintenance of renal perfusion. In these patients, administration of an NSAID may cause a dose-dependent reduction in prostaglandin formation and, secondarily, in renal blood flow, which may precipitate overt renal decompensation. Patients at greatest risk of this reaction are those with impaired renal function, dehydration, hypovolemia, heart failure, liver dysfunction, those taking diuretics and ACE inhibitors or ARBs, and the elderly. Discontinuation of NSAID therapy is usually followed by recovery to the pretreatment state.

SYMBRAVO is not recommended in patients with moderate to severe renal insufficiency and is contraindicated in patients with moderate to severe renal insufficiency who are at risk for renal failure due to volume depletion.

No information is available from controlled clinical studies regarding the use of meloxicam in patients with advanced renal disease. The renal effects of SYMBRAVO may hasten the progression of renal dysfunction in patients with pre-existing renal disease.

Correct volume status in dehydrated or hypovolemic patients prior to initiating SYMBRAVO. Monitor renal function in patients with renal or hepatic impairment, heart failure, dehydration, or hypovolemia during use of SYMBRAVO [see Drug Interactions (7.1)]. Avoid the use of SYMBRAVO in patients with advanced renal disease unless the benefits are expected to outweigh the risk of worsening renal function. If SYMBRAVO is used in patients with advanced renal disease, monitor patients for signs of worsening renal function [see Clinical Pharmacology (12.3)].

Hyperkalemia

Increases in serum potassium concentration, including hyperkalemia, have been reported with use of NSAIDs, even in some patients without renal impairment. In patients with normal renal function, these effects have been attributed to a hyporeninemic-hypoaldosteronism state.

5.12 Serious Skin Reactions

NSAIDs, including SYMBRAVO, can cause serious skin adverse reactions such as exfoliative dermatitis, Stevens-Johnson Syndrome (SJS), and toxic epidermal necrolysis (TEN), which can be fatal. NSAIDs can also cause fixed drug eruption (FDE). FDE may present as a more severe variant known as generalized bullous fixed drug eruption (GBFDE), which can be life-threatening. These serious events may occur without warning. Inform patients about the signs and symptoms of serious skin reactions, and to discontinue the use of SYMBRAVO at the first appearance of skin rash or any other sign of hypersensitivity. SYMBRAVO is contraindicated in patients with previous serious skin reactions to NSAIDs [see Contraindications (4)].

5.13 Drug Reaction with Eosinophilia and Systemic Symptoms (DRESS)

Drug Reaction with Eosinophilia and Systemic Symptoms (DRESS) has been reported in patients taking NSAIDs such as SYMBRAVO. Some of these events have been fatal or life-threatening. DRESS typically, although not exclusively, presents with fever, rash, lymphadenopathy, and/or facial swelling. Other clinical manifestations may include hepatitis, nephritis, hematological abnormalities, myocarditis, or myositis. Sometimes symptoms of DRESS may resemble an acute viral infection. Eosinophilia is often present. Because this disorder is variable in its presentation, other organ systems not noted here may be involved. It is important to note that early manifestations of hypersensitivity, such as fever or lymphadenopathy, may be present even though rash is not evident. If such signs or symptoms are present, discontinue SYMBRAVO and evaluate the patient immediately.

5.14 Fetal Toxicity

Premature Closure of Fetal Ductus Arteriosus

Avoid use of NSAIDs, including SYMBRAVO, in pregnant women at about 30 weeks gestation and later. NSAIDs, including SYMBRAVO, increase the risk of premature closure of the fetal ductus arteriosus at approximately this gestational age.

Oligohydramnios/Neonatal Renal Impairment

Use of NSAIDs, including SYMBRAVO, at about 20 weeks gestation or later in pregnancy may cause fetal renal dysfunction leading to oligohydramnios and, in some cases, neonatal renal impairment. These adverse outcomes are seen, on average, after days to weeks of treatment, although oligohydramnios has been infrequently reported as soon as 48 hours after NSAID initiation. Oligohydramnios is often, but not always, reversible with treatment discontinuation. Complications of prolonged oligohydramnios may, for example, include limb contractures and delayed lung maturation. In some postmarketing cases of impaired neonatal renal function, invasive procedures such as exchange transfusion or dialysis were required.

If NSAID treatment is necessary between about 20 weeks and 30 weeks gestation, limit SYMBRAVO use to the lowest effective dose and shortest duration possible.

Consider ultrasound monitoring of amniotic fluid if SYMBRAVO treatment extends beyond 48 hours. Discontinue SYMBRAVO if oligohydramnios occurs and follow up according to clinical practice [see Use in Specific Populations (8.1)].

5.15 Hematologic Toxicity

Anemia has occurred in NSAID-treated patients. This may be due to occult or gross blood loss, fluid retention, or an incompletely described effect on erythropoiesis. If a patient treated with SYMBRAVO has any signs or symptoms of anemia, monitor hemoglobin or hematocrit.

NSAIDs, including SYMBRAVO, may increase the risk of bleeding events. Co-morbid conditions such as coagulation disorders or concomitant use of warfarin, other anticoagulants, antiplatelet agents (e.g., aspirin), SSRIs and SNRIs may increase this risk. Monitor these patients for signs of bleeding [see Drug Interactions (7.1)].

5.16 Exacerbation of Asthma Related to Aspirin Sensitivity

A subpopulation of patients with asthma may have aspirin-sensitive asthma which may include chronic rhinosinusitis complicated by nasal polyps; severe, potentially fatal bronchospasm; and/or intolerance to aspirin and other NSAIDs. Because cross-reactivity between aspirin and other NSAIDs has been reported in such aspirin-sensitive patients, SYMBRAVO is contraindicated in patients with this form of aspirin sensitivity [see Contraindications (4)]. When SYMBRAVO is used in patients with preexisting asthma (without known aspirin sensitivity), monitor patients for changes in the signs and symptoms of asthma.

5.17 Medication Overuse Headache

Overuse of acute migraine drugs (e.g., ergotamine, triptans, opioids, or a combination of drugs for 10 or more days per month) may lead to exacerbation of headache (medication overuse headache). Medication overuse headache may present as migraine-like daily headaches, or as a marked increase in frequency of migraine attacks. Detoxification of patients, including withdrawal of the overused drugs, and treatment of withdrawal symptoms (which often includes a transient worsening of headache) may be necessary.

5.18 Serotonin Syndrome

Serotonin syndrome may occur with triptans, including SYMBRAVO particularly during co-administration with selective serotonin reuptake inhibitors (SSRIs), serotonin norepinephrine reuptake inhibitors (SNRIs), tricyclic antidepressants (TCAs), and MAO inhibitors (MAOIs). Serotonin syndrome symptoms may include mental status changes (e.g., agitation, hallucinations, coma), autonomic instability (e.g., tachycardia, labile blood pressure, hyperthermia), neuromuscular aberrations (e.g., hyperreflexia, incoordination) and/or gastrointestinal symptoms (e.g., nausea, vomiting, diarrhea). The onset of symptoms can occur within minutes to hours of receiving a new or a greater dose of a serotonergic medication. SYMBRAVO treatment should be discontinued if serotonin syndrome is suspected [see Drug Interactions (7.1), Patient Counseling Information (17)].

5.19 Masking of Inflammation and Fever

The pharmacological activity of SYMBRAVO in reducing inflammation, and possibly fever, may diminish the utility of diagnostic signs in detecting infections.

5.20 Laboratory Monitoring

Because serious GI bleeding, hepatotoxicity, and renal injury can occur without warning symptoms or signs, consider monitoring patients on long-term NSAID treatment with a complete blood count (CBC) and a chemistry profile periodically [see Warnings and Precautions (5.2, 5.8, 5.11]. Discontinue SYMBRAVO if GI bleeding occurs or if abnormal liver or renal tests persist or worsen.

6 ADVERSE REACTIONS

The following adverse reactions are discussed in more detail in other sections of the labeling:

- Cardiovascular Thrombotic Events and Myocardial Infarction [see Warnings and Precautions (5.1)]
- GI Bleeding, Ulceration, and Perforation [see Warnings and Precautions (5.2)]
- Arrhythmias [see Warnings and Precautions (5.3)]
- Cerebrovascular Events [see Warnings and Precautions (5.4)]
- Anaphylactic Reactions [see Warnings and Precautions (5.5)]
- Chest, Throat, Neck and/or Jaw Pain/Tightness/Pressure [see Warnings and Precautions (5.6)]
- Other Vasospasm Reactions [see Warnings and Precautions (5.7)]
- Hepatotoxicity [see Warnings and Precautions (5.8)]
- Hypertension/Increase in Blood Pressure [see Warnings and Precautions (5.9)]
- Heart Failure and Edema [see Warnings and Precautions (5.10)]
- Renal Toxicity and Hyperkalemia [see Warnings and Precautions (5.11)]
- Serious Skin Reactions [see Warnings and Precautions (5.12)]
- Drug Reaction with Eosinophilia and Systemic Symptoms (DRESS) [see Warnings and Precautions (5.13)]
- Fetal Toxicity [see Warnings and Precautions (5.14)]
- Hematologic Toxicity [see Warnings and Precautions (5.15)]
- Exacerbation of Asthma Related to Aspirin Sensitivity [see Warnings and Precautions (5.16)]
- Medication Overuse Headache [see Warnings and Precautions (5.17)]
- Serotonin Syndrome [see Warnings and Precautions (5.18)]

6.1 Clinical Trials Experience

Because clinical trials are conducted under widely varying conditions, adverse reaction rates observed in the clinical trials of a drug cannot be directly compared to rates in the clinical trials of another drug and may not reflect the rates observed in clinical practice.

In two randomized, double-blind, controlled trials in adults with migraine, a total of 581 patients received a single dose of SYMBRAVO after the onset of a migraine attack (Studies 1 and 2) [see Clinical Studies (14)]. The most common adverse reactions from these two trials after treatment with SYMBRAVO (incidence ≥1% and greater than placebo) are provided in Table 1.

Table 1: Incidence (≥1% and Greater than Placebo) of Adverse Reactions after a Single Dose of SYMBRAVO in Adults (Study 1 and Study 2)
 | SYMBRAVO N=581a % | Rizatriptan 10 mg; N=434b % | Meloxicam 20 mg; N=433b % | Placebo N=361a %
Somnolence | 2 | 2 | 2 | 1
Dizziness | 2 | 2 | 1 | 1
a Study 1 and Study 2 pooled
b Data from Study 1 only; Study 2 did not include arms with each individual component

Long-term safety was assessed in 706 patients dosing intermittently for up to 12 months in an open-label extension trial where patients treated at least 2 migraines per month with SYMBRAVO. Of these 706 patients, 496 patients were exposed to SYMBRAVO for at least 6 months, and 132 were exposed for at least 12 months, all of whom treated at least 2 migraine attacks per month, on average.

6.2 Postmarketing Experience

The following adverse reactions have been reported with the individual components of SYMBRAVO, meloxicam and rizatriptan, from postmarketing experience. Because these reactions are reported voluntarily from a population of unknown size, it is not always possible to reliably estimate their frequency or establish a causal relationship to drug exposure.

Meloxicam

Blood and Lymphatic System Disorders: Agranulocytosis

Hepatobiliary Disorders: Jaundice; liver failure

Psychiatric Disorders: Alterations in mood (such as mood elevation)

Renal and Urinary Disorders: Acute urinary retention; interstitial nephritis

Reproductive System and Breast Disorders: Infertility female

Skin and Subcutaneous Tissue Disorders: Anaphylactic reactions including shock; erythema multiforme; exfoliative dermatitis; Stevens-Johnson syndrome; fixed drug eruption (FDE); toxic epidermal necrolysis [see Warnings and Precautions (5.12)]

Rizatriptan

General: Allergic conditions including anaphylaxis/ anaphylactic reaction, angioedema, wheezing, and toxic epidermal necrolysis [see Contraindications (4)]

Neurological/Psychiatric: Seizure

Special Senses: Dysgeusia

7 DRUG INTERACTIONS

7.1 Drugs Having Clinically Important Interactions with SYMBRAVO

See Table 2 for clinically significant drug interactions with SYMBRAVO [see Clinical Pharmacology (12.3)].

Table 2: Clinically Important Drug Interactions with SYMBRAVO
Drugs That Interfere with Hemostasis
Clinical Impact | - Meloxicam and anticoagulants such as warfarin have a synergistic effect on bleeding. The concomitant use of meloxicam and anticoagulants have an increased risk of serious bleeding compared to the use of either drug alone. - Serotonin release by platelets plays an important role in hemostasis. Case-control and cohort epidemiological studies showed that concomitant use of drugs that interfere with serotonin reuptake and an NSAID may potentiate the risk of bleeding more than an NSAID alone.
Intervention | Monitor patients with concomitant use of SYMBRAVO with anticoagulants (e.g., warfarin), antiplatelet agents (e.g., aspirin), selective serotonin reuptake inhibitors (SSRIs), and serotonin norepinephrine reuptake inhibitors (SNRIs) for signs of bleeding [see Warnings and Precautions (5.15)]. Caution should be used when administering SYMBRAVO with warfarin since patients on warfarin may experience changes in International Normalized Ratio (INR) and an increased risk of bleeding complications when a new medication is introduced.
Aspirin
Clinical Impact | Controlled clinical studies showed that the concomitant use of NSAIDs and analgesic doses of aspirin does not produce any greater therapeutic effect than the use of NSAIDs alone. In a clinical study, the concomitant use of an NSAID and aspirin was associated with a significantly increased incidence of GI adverse reactions as compared to use of the NSAID alone [see Warnings and Precautions (5.2)].
Intervention | - Concomitant use of SYMBRAVO and analgesic doses of aspirin is not generally recommended because of the increased risk of bleeding [see Warnings and Precautions (5.15)]. - In the setting of concomitant use of low-dose aspirin for cardiac prophylaxis, monitor patients more closely for evidence of GI bleeding [see Warnings and Precautions (5.2)]. - Meloxicam in SYMBRAVO is not a substitute for low dose aspirin for cardiovascular protection.
SSRIs/SNRIs and Serotonin Syndrome
Clinical Impact | Cases of serotonin syndrome have been reported during co-administration of triptans and SSRIs or SNRIs [see Warnings and Precautions (5.18)].
Intervention | SYMBRAVO treatment should be discontinued if serotonin syndrome is suspected.
ACE Inhibitors, Angiotensin Receptor Blockers, and Beta-Blockers
Clinical Impact | - NSAIDs may diminish the antihypertensive effect of angiotensin converting enzyme (ACE) inhibitors, angiotensin receptor blockers (ARBs), or beta blockers. - In patients who are elderly, volume-depleted (including those on diuretic therapy), or have renal impairment, co-administration of an NSAID with ACE inhibitors or ARBs may result in deterioration of renal function, including possible acute renal failure. These effects are usually reversible. - Propranolol has been shown to increase the plasma AUC of rizatriptan.
Intervention | - During concomitant use of SYMBRAVO and ACE-inhibitors, ARBs, or beta blockers, monitor blood pressure to ensure that the desired blood pressure is obtained. - During concomitant use of SYMBRAVO and ACE-inhibitors or ARBs in patients who are elderly, volume-depleted, or have impaired renal function, monitor for signs of worsening renal function [see Warnings and Precautions (5.11)]. - When these drugs are administered concomitantly, patients should be adequately hydrated. Assess renal function at the beginning of the concomitant treatment and periodically thereafter. - The concomitant use of SYMBRAVO with propranolol is contraindicated.
Diuretics
Clinical Impact | Clinical studies, as well as postmarketing observations, showed that NSAIDs reduced the natriuretic effect of loop diuretics (e.g., furosemide) and thiazide diuretics in some patients. This effect has been attributed to the NSAID inhibition of renal prostaglandin synthesis. However, studies with furosemide agents and meloxicam have not demonstrated a reduction in natriuretic effect. Furosemide single and multiple dose pharmacodynamics and pharmacokinetics are not affected by multiple doses of meloxicam.
Intervention | During concomitant use of SYMBRAVO with diuretics, observe patients for signs of worsening renal function, in addition to assuring diuretic efficacy including antihypertensive effects [see Warnings and Precautions (5.11)].
Lithium
Clinical Impact | NSAIDs have produced elevations in plasma lithium levels and reductions in renal lithium clearance. This effect has been attributed to NSAID inhibition of renal prostaglandin synthesis.
Intervention | During concomitant use of SYMBRAVO and lithium, monitor patients for signs of lithium toxicity.
Methotrexate
Clinical Impact | Concomitant use of NSAIDs and methotrexate may increase the risk for methotrexate toxicity (e.g., neutropenia, thrombocytopenia, renal dysfunction).
Intervention | During concomitant use of SYMBRAVO and methotrexate, monitor patients for methotrexate toxicity.
Cyclosporine
Clinical Impact | Concomitant use of meloxicam and cyclosporine may increase cyclosporine’s nephrotoxicity.
Intervention | During concomitant use of SYMBRAVO and cyclosporine, monitor patients for signs of worsening renal function.
NSAIDs and Salicylates
Clinical Impact | Concomitant use of meloxicam with other NSAIDs or salicylates (e.g., diflunisal, salsalate) increases the risk of GI toxicity, with little or no increase in efficacy [see Warnings and Precautions (5.2)].
Intervention | The concomitant use of SYMBRAVO with other NSAIDs or salicylates is not recommended.
Pemetrexed
Clinical Impact | Concomitant use of meloxicam and pemetrexed may increase the risk of pemetrexed-associated myelosuppression, renal, and GI toxicity (see the pemetrexed prescribing information).
Intervention | During concomitant use of SYMBRAVO and pemetrexed, in patients with renal impairment whose creatinine clearance ranges from 45 to 79 mL/min, monitor for myelosuppression, renal and GI toxicity. Patients taking SYMBRAVO should interrupt dosing for at least five days before, the day of, and two days following pemetrexed administration. In patients with creatinine clearance below 45 mL/min, the concomitant administration of SYMBRAVO with pemetrexed is not recommended.
CYP2C9 Inhibitors
Clinical Impact | In vitro studies indicate that CYP2C9 (cytochrome P450 metabolizing enzyme) plays an important role in the metabolic pathway of meloxicam with a minor contribution of the CYP3A4 isozyme. Thus, concomitant usage of CYP2C9 inhibitors (e.g., amiodarone, fluconazole) may lead to abnormally high plasma levels of meloxicam due to reduced metabolic clearance [see Use in Specific Populations (8.8), Clinical Pharmacology (12.3, 12.5)].
Intervention | Use of SYMBRAVO in patients undergoing treatment with CYP2C9 inhibitors is not recommended.
Ergot-Containing Drugs
Clinical Impact | Ergot-containing drugs have been reported to cause prolonged vasospastic reactions.
Intervention | Because these effects may be additive with rizatriptan, use of ergotamine-containing or ergot-type medications (e.g., dihydroergotamine or methysergide) and SYMBRAVO within 24 hours is contraindicated [see Contraindications (4)].
5-HT1 Agonists
Clinical Impact | Vasospastic effects may be additive with co-administration within 24 hours of another 5-HT1 agonists.
Intervention | Use of SYMBRAVO within 24 hours of another 5HT1 agonist is contraindicated [see Contraindications (4)].
Monoamine Oxidase Inhibitors
Clinical Impact | MAO-A inhibitors increase the systemic exposure of rizatriptan and its metabolite.
Intervention | SYMBRAVO is contraindicated in patients taking MAO-A inhibitors and non-selective MAO inhibitors [see Contraindications (4)].

8 USE IN SPECIFIC POPULATIONS

8.1 Pregnancy

SYMBRAVO has not been studied in pregnant women. However, there are data pertaining to the use of the individual components, meloxicam and rizatriptan during pregnancy. These data are described below.

Risk Summary

In the U.S. general population, the estimated background risk of major birth defects and miscarriage in clinically recognized pregnancies is 2% to 4% and 15% to 20%, respectively. The reported rate of major birth defects among infants born to women with migraine range from 2.2% to 2.9% and the reported rate of miscarriage was 17%, which are similar to rates reported in women without migraine.

Meloxicam

Use of NSAIDs, including SYMBRAVO, can cause premature closure of the fetal ductus arteriosus and fetal renal dysfunction leading to oligohydramnios and, in some cases, neonatal renal impairment. Because of these risks, limit dose and duration of SYMBRAVO use between about 20 and 30 weeks of gestation, and avoid SYMBRAVO use at about 30 weeks of gestation and later in pregnancy [see Clinical Considerations, Data].

Premature Closure of Fetal Ductus Arteriosus

Use of NSAIDs, including SYMBRAVO, at about 30 weeks gestation or later in pregnancy increases the risk of premature closure of the fetal ductus arteriosus.

Oligohydramnios/Neonatal Renal Impairment

Use of NSAIDs at about 20 weeks gestation or later in pregnancy has been associated with cases of fetal renal dysfunction leading to oligohydramnios, and in some cases, neonatal renal impairment.

Data from observational studies regarding other potential embryofetal risks of NSAID use in women in the first or second trimesters of pregnancy are inconclusive.

In animal reproduction studies, embryofetal death was observed in rats and rabbits treated during the period of organogenesis with meloxicam at oral doses equivalent to 0.5 and 4.9 times, respectively, the maximum recommended human dose (MRHD) of 20 mg of meloxicam, based on body surface area (mg/m^2). Increased incidence of septal heart defects was observed in rabbits treated throughout embryogenesis with meloxicam at an oral dose equivalent to 59 times the MRHD of 20 mg of meloxicam on a mg/m^2 basis. In pre- and post-natal reproduction studies, there was an increased incidence of dystocia, delayed parturition, and decreased offspring survival at 0.06 times the MRHD of 20 mg of meloxicam on a mg/m^2 basis. No teratogenic effects were observed in rats and rabbits treated with meloxicam during organogenesis at an oral dose equivalent to 2 and 20 times, respectively, the MRHD of 20 mg of meloxicam on a mg/m^2 basis [see Data].

Based on animal data, prostaglandins have been shown to have an important role in endometrial vascular permeability, blastocyst implantation, and decidualization. In animal studies, administration of prostaglandin synthesis inhibitors, such as meloxicam, resulted in increased pre- and post-implantation loss. Prostaglandins also have been shown to have an important role in fetal kidney development. In published animal studies, prostaglandin synthesis inhibitors have been reported to impair kidney development when administered at clinically relevant doses.

Rizatriptan

Available human data on the use of rizatriptan in pregnant women are not sufficient to draw conclusions about drug-associated risk for major birth defects and miscarriage.

In animal studies, developmental toxicity was observed following oral administration of rizatriptan during pregnancy (decreased fetal body weight in rats) or throughout pregnancy and lactation (increased mortality, decreased body weight, and neurobehavioral impairment in rat offspring) at doses greater than the MRHD of 10 mg rizatriptan on a mg/m^2 basis [see Animal Data].

Clinical Considerations

Disease-Associated Maternal and/or Embryo/Fetal Risk

In women with migraine, there is an increased risk of adverse perinatal outcomes in the mother, including pre-eclampsia and gestational hypertension.

Fetal/Neonatal Adverse Reactions

Premature Closure of Fetal Ductus Arteriosus:

Avoid use of NSAIDs in women at about 30 weeks gestation and later in pregnancy, because NSAIDs, including SYMBRAVO, can cause premature closure of the fetal ductus arteriosus [see Data].

Oligohydramnios/Neonatal Renal Impairment

If an NSAID is necessary at about 20 weeks gestation or later in pregnancy, limit the use to the lowest effective dose and shortest duration possible. If SYMBRAVO treatment extends beyond 48 hours, consider monitoring with ultrasound for oligohydramnios. If oligohydramnios occurs, discontinue SYMBRAVO and follow up according to clinical practice [see Data].

Labor or Delivery

There are no studies on the effects of SYMBRAVO during labor or delivery. In animal studies, NSAIDs, including meloxicam, inhibit prostaglandin synthesis, cause delayed parturition, and increase the incidence of stillbirth.

Data

Human Data for Meloxicam

Premature Closure of Fetal Ductus Arteriosus:

Published literature reports that the use of NSAIDs at about 30 weeks of gestation and later in pregnancy may cause premature closure of the fetal ductus arteriosus.

Oligohydramnios/Neonatal Renal Impairment:

Published studies and postmarketing reports describe maternal NSAID use at about 20 weeks gestation or later in pregnancy associated with fetal renal dysfunction leading to oligohydramnios, and in some cases, neonatal renal impairment. These adverse outcomes are seen, on average, after days to weeks of treatment, although oligohydramnios has been infrequently reported as soon as 48 hours after NSAID initiation. In many cases, but not all, the decrease in amniotic fluid was transient and reversible with cessation of the drug. There have been a limited number of case reports of maternal NSAID use and neonatal renal dysfunction without oligohydramnios, some of which were irreversible. Some cases of neonatal renal dysfunction required treatment with invasive procedures, such as exchange transfusion or dialysis.

Methodological limitations of these postmarketing studies and reports include lack of a control group; limited information regarding dose, duration, and timing of drug exposure; and concomitant use of other medications. These limitations preclude establishing a reliable estimate of the risk of adverse fetal and neonatal outcomes with maternal NSAID use.

Because the published safety data on neonatal outcomes involved mostly preterm infants, the generalizability of certain reported risks to the full-term infant exposed to NSAIDs through maternal use is uncertain.

Human Data for Rizatriptan

In a pregnancy registry for rizatriptan users, no pattern of congenital anomalies or other adverse birth outcomes was identified over the period of 1998 to 2018. However, the lack of identification of any pattern should be viewed with caution, as the number of prospective reports with outcome information was low and did not provide sufficient power to detect an increased risk of individual birth defects associated with the use of rizatriptan. Additionally, there was significant loss to follow-up in the prospective pregnancy reports, further complicating this assessment of an association between rizatriptan and any pattern of congenital anomalies or other adverse birth outcomes.

In a study using data from the Swedish Medical Birth Register, live births to women who reported using triptans or ergots during pregnancy were compared with those of women who did not. Of the 157 births with first-trimester exposure to rizatriptan, 7 infants were born with malformations (relative risk 1.01 [95% CI: 0.40 to 2.08]). A study using linked data from the Medical Birth Registry of Norway to the Norwegian Prescription Database compared pregnancy outcomes in women who redeemed prescriptions for triptans during pregnancy, as well as a migraine disease comparison group who redeemed prescriptions for triptans before pregnancy only, compared with a population control group. Of the 310 women who redeemed prescriptions for rizatriptan during the first trimester, 10 had infants with major congenital malformations (OR 1.03 [95% CI: 0.55 to 1.93]), while for the 271 women who redeemed prescriptions for rizatriptan before, but not during, pregnancy, 12 had infants with major congenital malformations (OR 1.48 [95% CI: 0.83 to 2.64]), each compared with the population comparison group.

Animal Data

Animal reproduction studies have not been conducted for SYMBRAVO.

Meloxicam

Meloxicam was not teratogenic when administered to pregnant rats during fetal organogenesis at oral doses up to 4 mg/kg/day (2-fold greater than the MRHD of 20 mg of meloxicam on a mg/m^2 basis). Administration of meloxicam to pregnant rabbits throughout embryogenesis produced an increased incidence of septal defects of the heart at an oral dose of 60 mg/kg/day (59-fold greater than the MRHD of 20 mg of meloxicam on a mg/m^2 basis). The no effect level was 20 mg/kg/day (20-fold greater than the MRHD of 20 mg of meloxicam based on BSA conversion). In rats and rabbits, embryolethality occurred at oral meloxicam doses of 1 mg/kg/day and 5 mg/kg/day, respectively (0.5 and 4.9-fold greater, respectively, than the MRHD of 20 mg of meloxicam on a mg/m^2 basis) when administered throughout organogenesis.

Oral administration of meloxicam to pregnant rats during late gestation through lactation increased the incidence of dystocia, delayed parturition, and decreased offspring survival at meloxicam doses of 0.125 mg/kg/day or greater (0.06 times the MRHD of 20 mg of meloxicam based on BSA comparison).

Rizatriptan

When rizatriptan (0, 2, 10, or 100 mg/kg/day) was administered orally to pregnant rats throughout organogenesis, a decrease in fetal body weight was observed at the highest doses tested. The no-effect dose for adverse effects on embryofetal development was 10 mg/kg/day (10 times the MRHD of 10 mg of rizatriptan on a mg/m^2 basis). When rizatriptan (0, 5, 10, or 50 mg/kg/day) was administered orally to pregnant rabbits throughout organogenesis, no adverse fetal effects were observed. The highest dose tested of 50 mg/kg/day was 97 times the MRHD of 10 mg of rizatriptan on a mg/m^2 basis. Placental transfer of drug to the fetus was demonstrated in both species.

Oral administration of rizatriptan (0, 2, 10, or 100 mg/kg/day) to female rats prior to and during mating and continuing throughout gestation and lactation resulted in reduced body weight in offspring from birth and throughout lactation at all but the lowest dose tested (2 mg/kg/day). The no-effect dose (2 mg/kg/day) for adverse effects on postnatal development was 2 times the MRHD of 10 mg rizatriptan on a mg/m^2 basis.

Oral administration of rizatriptan (0, 5, 100, or 250 mg/kg/day) throughout organogenesis and lactation resulted in neonatal mortality, reduced body weight (which persisted into adulthood), and impaired neurobehavioral function in offspring at all but the lowest dose tested. The no-effect dose for adverse effects on postnatal development (5 mg/kg/day) was 5 times the MRHD of 10 mg rizatriptan on a mg/m^2 basis.

8.2 Lactation

Risk Summary

Meloxicam

There are no human data available on whether meloxicam is present in human milk, or on the effects on breastfed infants, or on milk production.

Rizatriptan

There are no adequate data on the presence of rizatriptan or any active metabolites in human milk, or on the effects of rizatriptan on the breastfed infant, or on milk production. Rizatriptan was excreted in rat milk with levels in milk approximately 6 times those in maternal plasma.

The developmental and health benefits of breastfeeding should be considered along with the mother’s clinical need for SYMBRAVO and any potential adverse effects on the breastfed infant from the SYMBRAVO or from the underlying maternal condition.

Data

Animal Data for Meloxicam

Meloxicam was present in the milk of lactating rats at concentrations higher than those in plasma.

Animal Data for Rizatriptan

Following oral administration of rizatriptan to lactating rats at a dose of 100 mg/kg/day, drug concentrations of rizatriptan in milk samples exceeded maternal plasma drug concentrations by approximately 6-fold.

8.3 Females and Males of Reproductive Potential

Infertility

Females

Based on the mechanism of action, the use of prostaglandin-mediated NSAIDs, including SYMBRAVO, may delay or prevent rupture of ovarian follicles, which has been associated with reversible infertility in some women. Published animal studies have shown that administration of prostaglandin synthesis inhibitors has the potential to disrupt prostaglandin-mediated follicular rupture required for ovulation. Small studies in women treated with NSAIDs have also shown a reversible delay in ovulation. Consider withdrawal of SYMBRAVO in women who have difficulties conceiving or who are undergoing investigation of infertility.

Males

Meloxicam in SYMBRAVO may compromise fertility in males of reproductive potential. In a published study, oral administration of meloxicam to male rats for 35 days resulted in decreased sperm count and motility and histopathological evidence of testicular degeneration at 0.5 times the MRHD on a mg/m^2 basis [see Nonclinical Toxicology (13.1)]. It is not known if these effects on fertility are reversible. The clinical relevance of these findings is unknown.

8.4 Pediatric Use

Safety and effectiveness of SYMBRAVO in pediatric patients have not been established.

8.5 Geriatric Use

Clinical studies of SYMBRAVO did not include subjects aged 65 and over to determine whether they respond differently from younger subjects.

Elderly patients, compared to younger patients, are at greater risk for NSAID-associated serious cardiovascular, gastrointestinal, hepatic, and/or renal adverse reactions. If the anticipated benefit for the elderly patient outweighs these potential risks, treat for the fewest number of days per month, as needed, and monitor patients for adverse effects [see Warnings and Precautions (5.1, 5.2, 5.8, 5.11)].

Geriatric patients who have other cardiovascular risk factors (e.g., diabetes, hypertension, smoking, obesity, strong family history of coronary artery disease) should have a cardiovascular evaluation prior to receiving SYMBRAVO [see Warnings and Precautions (5.1, 5.9)].

8.6 Renal Impairment

The use of SYMBRAVO, because of the meloxicam component, is contraindicated for patients with moderate to severe renal impairment who are at risk for renal failure due to volume depletion or for patients on hemodialysis, and is not recommended in patients with moderate to severe renal impairment [see Contraindications (4), Warnings and Precautions (5.11), Clinical Pharmacology (12.3)].

SYMBRAVO has not been studied in patients with renal impairment. The individual components, meloxicam and rizatriptan, have been studied and the results are described below.

Meloxicam

Pharmacokinetics of meloxicam in elderly subjects with mild renal impairment is similar to healthy young subjects. Patients with moderate or severe renal impairment have not been studied. Meloxicam is not dialyzable.

Rizatriptan

In patients with renal impairment (creatinine clearance 10-60 mL/min/1.73 m^2), the AUC0-inf of rizatriptan was not significantly different from that in subjects with normal renal function. In hemodialysis patients, (creatinine clearance <2 mL/min/1.73 m^2), however, the AUC for rizatriptan was greater than that in patients with normal renal function. Patients with severe renal impairment have not been studied [see Clinical Pharmacology (12.3)].

8.7 Hepatic Impairment

Use SYMBRAVO, because of the meloxicam component, with caution in patients with hepatic impairment, and monitor for adverse reactions when used in patients with severe hepatic impairment.

SYMBRAVO has not been studied in patients with hepatic impairment. The individual components, meloxicam and rizatriptan, have been studied and the results are described below.

Meloxicam

Following oral administration of meloxicam, patients with mild to moderate hepatic impairment had no marked differences in plasma concentrations. Patients with severe hepatic impairment have not been adequately studied. Meloxicam is significantly metabolized in the liver and hepatotoxicity may occur [see Warnings and Precautions (5.8), Clinical Pharmacology (12.3)].

Rizatriptan

Following oral administration of rizatriptan in patients with hepatic impairment caused by mild to moderate alcoholic cirrhosis of the liver, plasma concentrations of rizatriptan were similar in patients with mild hepatic impairment and greater in patients with moderate hepatic impairment, compared to a control group of subjects with normal hepatic function [see Clinical Pharmacology (12.3)].

8.8 Poor Metabolizers of CYP2C9 Substrates

In patients who are known or suspected to be poor CYP2C9 metabolizers based on genotype or previous history/experience with other CYP2C9 substrates (e.g., warfarin and phenytoin), the use of SYMBRAVO is not recommended as they may have abnormally high plasma levels due to reduced metabolic clearance of meloxicam. If SYMBRAVO is used in patients who are poor CYP2C9 metabolizers, monitor for adverse reactions.

10 OVERDOSAGE

No overdoses of SYMBRAVO were reported during clinical trials in adults. Evaluation and treatment of SYMBRAVO overdose is based on experience with the individual components, meloxicam and rizatriptan.

In case of an overdosage, discontinue SYMBRAVO and contact a regional poison control center at 1-800-222-1222.

Overdose of Meloxicam

Symptoms following acute meloxicam overdoses have been typically limited to lethargy, drowsiness, nausea, vomiting, and epigastric pain, which have been generally reversible with supportive care. Gastrointestinal bleeding has occurred. Hypertension, acute renal failure, respiratory depression and coma have occurred, but were rare [see Warnings and Precautions (5.2, 5.9, 5.11, 5.15)].

Manage patients with symptomatic and supportive care following a meloxicam overdosage. There are no specific antidotes. Consider emesis and/or activated charcoal (60 to 100 grams in adults, 1 to 2 grams per kg of body weight in pediatric patients) and/or osmotic cathartic in symptomatic patients seen within four hours of ingestion or in patients with a large overdosage (5 to 10 times the recommended dosage). Forced diuresis, alkalinization of urine, hemodialysis, or hemoperfusion may be employed but are not likely to be useful due to high protein binding.

There is limited experience with meloxicam overdose. In four reported cases of meloxicam overdose, patients took 6- to 11-times the highest available oral dose of meloxicam tablets (15 mg); all recovered. Cholestyramine is known to accelerate the clearance of meloxicam. Accelerated removal of meloxicam by 4 g doses of cholestyramine given three times a day was demonstrated in a clinical trial. Administration of cholestyramine may be useful following an overdosage.

Overdose of Rizatriptan

In a clinical pharmacology study in which 12 adult subjects received rizatriptan at total cumulative doses of 80 mg (given within four hours), two of the subjects experienced syncope, dizziness, bradycardia including third degree AV block, vomiting, and/or incontinence.

Based on the pharmacology of rizatriptan, hypertension or myocardial ischemia could occur after overdosage. Gastrointestinal decontamination, (i.e., gastric lavage followed by activated charcoal) should be considered in patients suspected of an overdose with rizatriptan. Clinical and electrocardiographic monitoring should be continued for at least 12 hours, even if clinical symptoms are not observed. The effects of hemo- or peritoneal dialysis on serum concentrations of rizatriptan are unknown.

11 DESCRIPTION

SYMBRAVO contains meloxicam, a nonsteroidal anti-inflammatory drug (NSAID), and rizatriptan (as rizatriptan benzoate), a selective 5-HT1B/1D receptor agonist.

Meloxicam

Meloxicam has the molecular formula C14 H13 N3 O4 S2 and is chemically designated as 4-hydroxy-2-methyl-N-(5 methyl-2-thiazolyl)-2H-1,2-benzothiazine-3-carboxamide-1,1-dioxide. It has a molecular weight of 351.4 g/mole.

The structural formula is:

Meloxicam is a pastel yellow solid, practically insoluble in water, with higher solubility observed in strong acids and bases. It is very slightly soluble in methanol. Meloxicam has an apparent partition coefficient (log P) = 0.1 in n-octanol/buffer pH 7.4. Meloxicam has pKa values of 1.1 and 4.2.

Rizatriptan

Rizatriptan benzoate has the molecular formula C15H19N5·C7H6O2 and is chemically designated as N,N-dimethyl-5-(1H-1,2,4-triazol-1-ylmethyl)-1H indole-3 ethanamine monobenzoate. The molecular weight of the free base rizatriptan is 269.4 g/mole. The structural formula is:

Rizatriptan benzoate is a white to off-white, crystalline solid that is soluble in water at about 42 mg per mL (expressed as free base) at 25°C.

Each SYMBRAVO tablet for oral administration contains 20 mg of meloxicam and 10 mg of rizatriptan (equivalent to 14.5 mg of rizatriptan benzoate). Each tablet also contains the excipients colloidal silicon dioxide, crospovidone, magnesium stearate, microcrystalline cellulose, partially hydrolyzed polyvinyl alcohol, polyethylene glycol, povidone, pregelatinized starch, sodium bicarbonate, sulfobutyl-ether-ß-cyclodextrin sodium, talc, and titanium dioxide.

12 CLINICAL PHARMACOLOGY

12.1 Mechanism of Action

SYMBRAVO contains meloxicam and rizatriptan.

Meloxicam has analgesic, anti-inflammatory, and antipyretic properties. The mechanism of action of meloxicam, like that of other NSAIDs, is not completely understood but involves inhibition of cyclooxygenase (COX-1 and COX-2).

Meloxicam is a potent inhibitor of prostaglandin synthesis in vitro. Meloxicam concentrations reached during therapy have produced in vivo effects. Prostaglandins sensitize afferent nerves and potentiate the action of bradykinin in inducing pain in animal models. Prostaglandins are mediators of inflammation. Because meloxicam is an inhibitor of prostaglandin synthesis, its mode of action may be due to a decrease of prostaglandins in peripheral tissues.

Rizatriptan binds with high affinity to human cloned 5-HT1B/1D receptors. Rizatriptan presumably exerts its therapeutic effects in the treatment of migraine headache by binding to 5-HT1B/1D receptors located on intracranial blood vessels and sensory nerves of the trigeminal system.

12.2 Pharmacodynamics

Cardiac Electrophysiology

Rizatriptan

The effects of rizatriptan on QT prolongation have not been studied; however, arrhythmias have occurred after administration of 5-HT1 agonists [see Warnings and Precautions (5.3)].

Blood Pressure

Rizatriptan

Significant elevation in blood pressure, including hypertensive crisis, has been reported in patients treated with rizatriptan, with and without a history of hypertension [see Warnings and Precautions (5.9)].

12.3 Pharmacokinetics

SYMBRAVO is a combination of rizatriptan and meloxicam. Meloxicam when given as SYMBRAVO has a mean Cmax of approximately 2,900 ng/mL and a mean AUC0-24 of approximately 33,000 ng*hr/mL. Rizatriptan when given as SYMBRAVO has a mean Cmax of 32 ng/mL and a mean AUC0-24 of 83 ng*hr/mL.

Absorption

After oral administration of a single dose of SYMBRAVO under fasted conditions, the median Tmax for the meloxicam component is 0.88 hours, which is less than oral meloxicam tablets (Tmax of 4-5 hours). The median Tmax for the rizatriptan component is 0.75 hours.

Effect of Food

The exposures of meloxicam and rizatriptan were comparable after administration of SYMBRAVO in the fasted and fed states.Administration of SYMBRAVO after a high-fat, high-calorie meal decreased the exposures of meloxicam by approximately 7% for AUC0-24 and 27% for Cmax and increased the AUC0-24 of rizatriptan by approximately 10% with no significant change in Cmax. Food intake delayed the time to maximal plasma concentration for both meloxicam (from 0.88 hours to 5 hours) and rizatriptan (from 0.75 hours to 1.5 hours). Therapeutic concentrations of meloxicam were achieved within 1.5 hours with co-administration of food [see Dosage and Administration (2.2)].

Distribution

Meloxicam

The apparent volume of distribution during the terminal elimination phase (Vz) of meloxicam is approximately 10 L.

Meloxicam is approximately 99.4% bound to human plasma proteins (primarily albumin) within the therapeutic dose range. The fraction of protein binding is independent of drug concentration, over the clinically relevant concentration range, but decreases to approximately 99% in patients with renal disease. Meloxicam penetration into human red blood cells, after oral dosing, is less than 10%. Following a radiolabeled dose, over 90% of the radioactivity detected in the plasma was present as unchanged meloxicam.

Rizatriptan

The mean volume of distribution of rizatriptan is approximately 140 liters in male subjects and 110 liters in female subjects. Rizatriptan is minimally bound (14%) to plasma proteins.

Elimination

Metabolism

Meloxicam

Meloxicam is extensively metabolized in the liver. Meloxicam metabolites include 5'-carboxy meloxicam (60% of dose), from cytochrome P450 (CYP) mediated metabolism formed by oxidation of an intermediate metabolite, 5'-hydroxymethyl meloxicam, which is also excreted to a lesser extent (9% of dose). In vitro studies indicate that CYP2C9 plays an important role in this metabolic pathway with a minor contribution of the CYP3A4 isozyme. Patients’ peroxidase activity is probably responsible for the other two metabolites, which account for 16% and 4% of the administered dose, respectively. The four metabolites are not known to have any in vivo pharmacological activity.

Rizatriptan

The primary route of rizatriptan metabolism is via oxidative deamination by monoamine oxidase-A (MAO-A) to the indole acetic acid metabolite, which is not active at the 5-HT1B/1D receptor. N-monodesmethyl-rizatriptan, a metabolite with activity similar to that of the parent compound at the 5-HT1B/1D receptor, is formed to a minor degree. Plasma concentrations of N-monodesmethyl-rizatriptan are approximately 14% of those of parent compound, and it is eliminated at a similar rate. Other minor metabolites, the N-oxide, the 6-hydroxy compound, and the sulfate conjugate of the 6-hydroxy metabolite are not active at the 5-HT1B/1D receptor.

After administration of SYMBRAVO, mean elimination half-life is approximately 18 hours for meloxicam and 2 hours for rizatriptan.

Excretion

Meloxicam

Meloxicam excretion is predominantly in the form of metabolites and occurs to equal extents in the urine and feces. Only traces of the unchanged parent compound are excreted in the urine (0.2%) and feces (1.6%). The extent of the urinary excretion was confirmed for unlabeled multiple 7.5 mg doses: 0.5%, 6%, and 13% of the dose were found in urine in the form of meloxicam, and the 5'-hydroxymethyl and 5'-carboxy metabolites, respectively. There is significant biliary and/or enteral secretion of the drug. This was demonstrated when oral administration of cholestyramine following a single intravenous dose of meloxicam decreased the AUC of meloxicam by 50%. The mean elimination half-life (t1/2) ranges from 15 hours to 20 hours. Plasma clearance ranges from 7 to 9 mL/min.

Rizatriptan

The total radioactivity of the administered dose recovered over 120 hours in urine and feces was 82% and 12%, respectively, following a single 10 mg oral administration of ^14C-rizatriptan. Following oral administration of ^14C-rizatriptan, rizatriptan accounted for about 17% of circulating plasma radioactivity. Approximately 14% of an oral dose is excreted in urine as unchanged rizatriptan while 51% is excreted as indole acetic acid metabolite, indicating substantial first pass metabolism. The plasma half-life of rizatriptan in males and females averages 2-3 hours.

Cytochrome P450 Isoforms

Rizatriptan is not an inhibitor of the activities of human liver cytochrome P450 isoforms 3A4/5, 1A2, 2C9, 2C19, or 2E1; rizatriptan is a competitive inhibitor (Ki=1400 nM) of cytochrome P450 2D6, but only at high, clinically irrelevant concentrations.

Specific Populations

Studies have not been conducted to assess the pharmacokinetics of SYMBRAVO in geriatric patients or in patients with renal or hepatic impairment.

Based on population pharmacokinetics analyses, age and gender do not have a clinically meaningful effect on the pharmacokinetics of meloxicam.

Geriatric Patients

Rizatriptan pharmacokinetics in healthy elderly volunteers without migraine (age 65-77 years) were similar to those in younger volunteers without migraine (age 18-45 years).

Male and Female Patients

The mean AUC0-∞ and Cmax of rizatriptan (10 mg orally) were about 30% and 11% higher in females as compared to males, respectively, while Tmax occurred at approximately the same time.

Patients with Renal Impairment

Meloxicam

The pharmacokinetics of meloxicam have been investigated in elderly subjects with mild renal impairment (eGFR 60 – 90) compared to young healthy volunteers. A 5% and 7% increase of Cmax and AUC, respectively, was observed in elderly subjects with mild renal impairment. Use of meloxicam in patients with moderate or severe renal impairment have not been studied [see Use in Specific Populations (8.6)].

Rizatriptan

In patients with renal impairment (creatinine clearance 10-60 mL/min/1.73 m^2), the AUC0-∞ of rizatriptan was not significantly different from that in subjects with normal renal function. In hemodialysis patients, (creatinine clearance <2 mL/min/1.73 m^2), however, the AUC for rizatriptan was approximately 44% greater than that in patients with normal renal function. Use of rizatriptan in patients with moderate and severe renal impairment have not been adequately studied.

Patients with Hepatic Impairment

Meloxicam

Following a single 15 mg dose of meloxicam tablets there was no marked difference in plasma concentrations in patients with mild (Child-Pugh Class I) or moderate (Child-Pugh Class II) hepatic impairment compared to healthy volunteers. Protein binding of meloxicam was not affected by hepatic impairment. Use of meloxicam in patients with severe hepatic impairment (Child-Pugh Class III) have not been adequately studied [see Warnings and Precautions (5.8), Use in Specific Populations (8.7)].

Rizatriptan

Following oral administration of rizatriptan in patients with hepatic impairment caused by mild to moderate alcoholic cirrhosis of the liver, plasma concentrations of rizatriptan were similar in patients with mild hepatic impairment compared to a control group of subjects with normal hepatic function; plasma concentrations of rizatriptan were approximately 30% greater in patients with moderate hepatic impairment.

Drug Interaction Studies

Aspirin: When NSAIDs were administered with aspirin, the protein binding of NSAIDs were reduced, although the clearance of free NSAID was not altered. The clinical significance of this interaction is not known [see Drug Interactions (7.1)].

Cholestyramine: Pretreatment for four days with cholestyramine significantly increased the clearance of meloxicam by 50%. This resulted in a decrease in t1/2, from 19.2 hours to 12.5 hours, and a 35% reduction in AUC. This suggests the existence of a recirculation pathway for meloxicam in the gastrointestinal tract. The clinical relevance of this interaction has not been established.

Cimetidine: Concomitant administration of 200 mg cimetidine four times daily did not alter the single-dose pharmacokinetics of 30 mg meloxicam.

Digoxin: Meloxicam tablets 15 mg once daily for 7 days did not alter the plasma concentration profile of digoxin after β-acetyldigoxin administration for 7 days at clinical doses. In vitro testing found no protein binding drug interaction between digoxin and meloxicam [see Drug Interactions (7.1)].

Lithium: In a study conducted in healthy subjects, mean pre-dose lithium concentration and AUC were increased by 21% in subjects receiving lithium doses ranging from 804 to 1072 mg twice daily with meloxicam tablets 15 mg once per day every day as compared to subjects receiving lithium alone [see Drug Interactions (7.1)].

Methotrexate: A study in 13 rheumatoid arthritis (RA) patients evaluated the effects of multiple oral doses of meloxicam on the pharmacokinetics of methotrexate taken once weekly. Meloxicam did not have a significant effect on the pharmacokinetics of single doses of methotrexate. In vitro, methotrexate did not displace meloxicam from its human serum binding sites [Drug Interactions (7.1)].

Monoamine Oxidase Inhibitors: Rizatriptan is principally metabolized via monoamine oxidase, ‘A’ subtype (MAO-A). Plasma concentrations of rizatriptan may be increased by drugs that are selective MAO-A inhibitors (e.g., moclobemide) or nonselective MAO inhibitors [type A and B] (e.g., isocarboxazid, phenelzine, tranylcypromine, and pargyline). In a drug interaction study, when 10 mg of rizatriptan was administered to subjects (n=12) receiving concomitant therapy with the selective, reversible MAO-A inhibitor, moclobemide 150 mg three times a day, there were mean increases in rizatriptan AUC and Cmax of 119% and 41% respectively; and the AUC of the active N-monodesmethyl metabolite of rizatriptan was increased more than 400%. The interaction would be expected to be greater with irreversible MAO inhibitors. No pharmacokinetic interaction is anticipated in patients receiving selective MAO-B inhibitors [Contraindications (4)].

Nadolol/Metoprolol: In a drug interactions study, effects of multiple doses of nadolol 80 mg or metoprolol 100 mg every 12 hours on the pharmacokinetics of a single dose of 10 mg rizatriptan were evaluated in healthy subjects (n=12). No pharmacokinetic interactions were observed.

Oral Contraceptives: In a study of concurrent administration of an oral contraceptive during 6 days of administration of rizatriptan (10‑30 mg/day) in healthy female volunteers (n=18), rizatriptan did not affect plasma concentrations of ethinyl estradiol or norethindrone.

Propranolol: In a study of concurrent administration of propranolol 240 mg/day and a single dose of rizatriptan 10 mg in healthy adult subjects (n=11), mean plasma AUC for rizatriptan was increased by 70% during propranolol administration, and a 4-fold increase was observed in one subject. The AUC of the active N-monodesmethyl metabolite of rizatriptan was not affected by propranolol [see Contraindications (4) and Drug Interactions (7.1)].

Paroxetine: In a study of the interaction between the SSRI paroxetine 20 mg/day for two weeks and a single dose of rizatriptan 10 mg in healthy subjects (n=12), neither the plasma concentrations of rizatriptan nor its safety profile were affected by paroxetine [see Warnings and Precautions (5.18), Drug Interactions (7.1), and Patient Counseling Information (17)].

Warfarin: The effect of meloxicam tablets on the anticoagulant effect of warfarin was studied in a group of healthy subjects receiving daily doses of warfarin that produced an International Normalized Ratio (INR) between 1.2 and 1.8. In these subjects, meloxicam did not alter warfarin pharmacokinetics and the average anticoagulant effect of warfarin as determined by prothrombin time. However, one subject showed an increase in INR from 1.5 to 2.1 [see Drug Interactions (7.1)].

12.5 Pharmacogenomics

CYP2C9 activity is reduced in individuals with genetic variants such as CYP2C9*2 and CYP2C9*3 polymorphisms. Limited data from three published reports showed that meloxicam AUC was substantially higher in individuals with reduced CYP2C9 activity, particularly in poor metabolizers (e.g., *3/*3), compared to normal metabolizers (*1/*1). The frequency of CYP2C9 poor metabolizer genotypes varies based on racial/ethnic background but is generally present in <5% of the population [see Use in Specific Populations (8.8)].

13 NONCLINICAL TOXICOLOGY

13.1 Carcinogenesis, Mutagenesis, Impairment of Fertility

The potential effects of the SYMBRAVO on carcinogenesis, mutagenesis, or impairment of fertility have not been studied. However, the individual components, meloxicam and rizatriptan, have been studied and the results of these studies are described below.

Carcinogenesis

Meloxicam

There was no increase in tumor incidence in long-term carcinogenicity studies in rats (104 weeks) and mice (99 weeks) administered meloxicam at oral doses up to 0.8 mg/kg/day in rats and up to 8.0 mg/kg/day in mice (up to 0.4 and 2 times, respectively, the MRHD of 20 mg/day of meloxicam on a mg/m^2 basis).

Rizatriptan

Oral carcinogenicity studies of rizatriptan were conducted in mice (100 weeks) and rats (106 weeks) at doses of up to 125 mg/kg/day (up to 60 and 120 times, respectively, the MRHD of 10 mg of rizatriptan on a mg/m^2 basis). There was no evidence of an increase in tumor incidence related to rizatriptan in either species.

Mutagenesis

Meloxicam

Meloxicam was not mutagenic in an Ames assay. Meloxicam was not clastogenic in an in vitro chromosome aberration assay with human lymphocytes and an in vivo micronucleus assay in mouse bone marrow.

Rizatriptan

Rizatriptan was neither mutagenic nor clastogenic in a battery of in vitro and in vivo genetic toxicity studies, including: the microbial mutagenesis (Ames) assay, in vitro mammalian cell mutagenesis and chromosomal aberration assays, and the in vivo chromosomal aberration assay in mouse.

Impairment of fertility

Meloxicam

Meloxicam did not impair male and female fertility in rats at oral doses up to 9 mg/kg/day in males and 5 mg/kg/day in females (up to 4.4 and 2.4 times greater, respectively, than the MRHD of 20 mg of meloxicam on a mg/m^2 basis).

In a published study, oral administration of 1 mg/kg (0.5 times the MRHD on a mg/m^2 basis) meloxicam to male rats for 35 days resulted in decreased sperm count and motility and histopathological evidence of testicular degeneration. The clinical relevance of these findings is unknown.

Rizatriptan

Oral administration of rizatriptan (0, 2, 10, or 100 mg/kg/day) to female rats prior to and during mating and continuing throughout gestation and lactation resulted in no effect on fertility; however, altered estrous cyclicity and delays in time to mating were observed at the highest dose tested. The no-effect dose for reproductive toxicity was approximately 10 mg/kg/day (10 times the MRHD of 10 mg rizatriptan on a mg/m^2 basis). Oral administration of rizatriptan (0, 5, 35, or 250 mg/kg/day) to male rats prior to and during mating resulted in no impairment of fertility or reproductive performance. The highest dose tested (250 mg/kg/day) was 242 times the MRHD of 10 mg rizatriptan on a mg/m^2 basis.

14 CLINICAL STUDIES

Study 1: Efficacy Trial

The efficacy of SYMBRAVO for the acute treatment of migraine with or without aura in adults was demonstrated in one randomized, double-blind, controlled trial [Study 1 (NCT03896009)]. SYMBRAVO demonstrated an effect on headache pain freedom and most bothersome symptom (MBS) freedom at two hours after dosing, compared to placebo. Among patients who selected an MBS, the most commonly selected symptom was photophobia (61%), followed by nausea (20%), and phonophobia (19%).

In Study 1, 1,594 patients with a history of migraine with or without aura, according to the International Classification of Headache Disorders (ICHD-3) diagnostic criteria, were randomized to receive either SYMBRAVO (N=456), 10 mg rizatriptan (N=456), 20 mg meloxicam (matching the formulation of the meloxicam used in SYMBRAVO) (N=455), or placebo (N=227). Patients were instructed to treat a migraine of moderate to severe pain intensity with a single dose of medication. Rescue medication (including triptans and NSAIDs) was allowed 2 hours after the initial treatment; however, ergots were not allowed within 24 hours before or after study drug administration, and opioids were not allowed for the duration of the study. Patients were 83% female and 17% male, predominantly White (77%), with a mean age of 41.2 years (range 18-67). Approximately 7% of patients were taking preventive medications for migraine at baseline.

The primary efficacy analyses were conducted in patients who treated a migraine with moderate to severe pain. Pain freedom was defined as a reduction of moderate or severe headache pain to no headache pain, and MBS freedom was defined as the absence of the self-identified MBS (i.e., photophobia, phonophobia, or nausea). The percentage of patients achieving headache pain freedom and MBS freedom 2 hours after a single dose was statistically significantly greater among patients who received SYMBRAVO compared to those who received placebo (Table 3).

The key secondary endpoint of percentage of patients who experienced sustained pain freedom up to 24 hours (pain free from 2 hours through 24 hours postdose without use of other medications) was statistically significantly greater among patients who received a single dose of SYMBRAVO (16.1%) compared to those who received meloxicam (9%; p=0.001), or rizatriptan (11%; p=0.038).

Additional secondary endpoints included pain relief (reduction in migraine pain intensity from moderate or severe to mild or no headache pain) and the ability to perform normal daily activities at 2 hours after dosing. The ability to perform normal daily activities at two hours after dosing was derived from a single item questionnaire, which asked patients to select one response on a 4-point scale; normal function, mild impairment, severe impairment, or required bedrest. A statistically significantly greater percentage of participants who received SYMBRAVO achieved pain relief at 2 hours after dosing and were able to perform normal daily activities at 2 hours after dosing when compared to placebo (Table 3).

Table 3: Migraine Efficacy Endpoints for SYMBRAVO (Study 1)a
 | SYMBRAVO; (N=428) | Rizatriptan; (N=419) | Meloxicam; (N=421) | Placebo; (N=209)
Co-Primary Endpoints
Pain Free at Hour 2 | 19.9%b | 17.4% | 11.6% | 6.7%
MBS Free at Hour 2 | 36.9%b | 35.8% | 32.5% | 24.4%
Key-Secondary Endpoint
24 Hour Sustained Pain; Freedom | 16.1%c | 11.2% | 8.8% | 5.3%
Other Secondary Endpoints
Pain Relief at Hour 2 | 69.2%b | 65.6% | 62.0% | 54.5%
Able to Perform Normal Daily Activities at Hour 2 | 32.0%b | 30.3% | 24.5% | 21.1%
a p-values provided only for prespecified comparisons.
b p<0.01 versus placebo.
c p<0.05 versus rizatriptan, and meloxicam.

Use of rescue medication within 24 hours was also evaluated. There was a numerically lower percentage of patients who received SYMBRAVO and used a rescue medication within 24 hours (23%) vs rizatriptan (35%), meloxicam (35%), and placebo (44%).

Figure 1 presents the percentage of patients achieving migraine pain freedom within 2 hours following treatment in Study 1.

Figure 1: Percentage of Patients Achieving Migraine Pain Freedom Within 2 Hours in Study 1

Figure 2 presents the percentage of patients achieving MBS freedom within 2 hours following treatment Study 1.

Figure 2: Percentage of Patients Achieving MBS Freedom Within 2 Hours in Study 1

The incidence of photophobia and phonophobia at 2 hours was reduced following administration of SYMBRAVO as compared to placebo, with 33.5% and 23.5%. of subjects, respectively, reporting absence of photophobia, and 40.0% vs 18.6% of patients, respectively, reporting absence of phonophobia.

Study 2: Treatment of a Migraine When Mild in Severity

In Study 2 (NCT04163185), 302 patients with a history of migraine with or without aura, according to the ICHD-3 diagnostic criteria, were randomized to either SYMBRAVO (N=152) or placebo (N=150). Patients were instructed to treat a migraine when the initial pain was mild, with a single dose of medication. Rescue medication was allowed 2 hours after the initial treatment. Patients were 85.4% female and 14.6% male, predominantly White (83.1%), with a mean age of 41.5 years (range 19-65), and a mean BMI of 28.5 kg/m^2 (range 17.2-39.9). Approximately 6.4% of patients were taking preventive medications for migraine at baseline.

The primary efficacy analyses were conducted in patients who treated a migraine with initial pain that was mild. The percentage of patients achieving headache pain freedom and MBS freedom 2 hours after a single dose was statistically significantly greater among patients who received SYMBRAVO compared to those who received placebo (Table 4). Pain freedom at 2 hours was 32.6% in the SYMBRAVO treated group, compared to 16.3% in placebo (p=0.002). MBS freedom at 2 hours was 43.9% in the SYMBRAVO treated group, compared to 26.7% in the placebo group (p=0.003) (Table 4).

Table 4: Migraine Efficacy Endpoints for SYMBRAVO in Treatment of a Migraine at Mild Pain Intensity (Study 2)
 | SYMBRAVO | Placebo
Pain Free at 2 hours
N | 132 | 135
% Responder | 32.6% | 16.3%
p-value | 0.002
Most Bothersome Symptom Free at 2 hours
N | 132 | 135
% Responder | 43.9% | 26.7%
p-value | 0.003

In Study 2, the percentage of patients with sustained pain freedom from 2 to 24 hours was numerically greater in SYMBRAVO than placebo (22.7% vs 12.6%) and rescue medication use within 24 hours was also numerically less in SYMBRAVO than placebo (15.2% vs 42.2%).

Figure 3 presents the percentage of patients achieving migraine pain freedom within 2 hours following treatment Study 2.

Figure 3: Percentage of Patients Achieving Pain Freedom Within 2 Hours in Study 2

Figure 4 presents the percentage of patients achieving MBS freedom within 2 hours following treatment Study 2.

Figure 4: Patients of Patients Achieving MBS Freedom Within 2 Hours in Study 2

The incidence of photophobia and phonophobia at 2 hours was reduced following administration of SYMBRAVO as compared to placebo, with 43.2% vs 20.5%. of patients, respectively, reporting absence of photophobia, and 43.8% vs 25.0% of patients, respectively, reporting absence of phonophobia.

16 HOW SUPPLIED/STORAGE AND HANDLING

16.1 How Supplied

SYMBRAVO tablets are white, modified capsule-shaped, film-coated and debossed with "MXRZ" on one side and "20/10" on the other. SYMBRAVO is supplied in the following package configuration:

Package Configuration | Strength | NDC Code
Bottles of 9 tablets | meloxicam 20 mg and rizatriptan 10 mg | 81968-020-09

16.2 Storage and Handling

Store SYMBRAVO in the original bottle at 20°C to 25°C (68°F to 77°F), excursions permitted to 15°C to 30°C (59°F to 86°F) [see USP Controlled Room Temperature].

17 PATIENT COUNSELING INFORMATION

Advise the patient to read the FDA-approved patient labeling (Medication Guide).

Cardiovascular Thrombotic Effects

Advise patients to be alert for the symptoms of cardiovascular thrombotic events, including chest pain, shortness of breath, weakness, or slurring of speech, and to report any of these symptoms to their healthcare provider immediately [see Warnings and Precautions (5.1)].

Risk of Myocardial Ischemia and/or Infarction, Prinzmetal’s Angina, Other Vasospasm-Related Events, and Cerebrovascular Events

Inform patients that rizatriptan, a component of SYMBRAVO, may cause serious cardiovascular side effects such as myocardial infarction or stroke. Although serious cardiovascular events can occur without warning symptoms, patients should be alert for the signs and symptoms of chest pain, shortness of breath, weakness, slurring of speech, and should ask for medical advice when observing any indicative sign or symptoms. Patients should be apprised of the importance of this follow-up [see Warnings and Precautions (5.1, 5.3, 5.4, 5.6, 5.7)].

Gastrointestinal Bleeding, Ulceration, and Perforation

Advise patients to report symptoms of ulcerations and bleeding, including epigastric pain, dyspepsia, melena, and hematemesis to their healthcare provider. In the setting of concomitant use of low-dose aspirin for cardiac prophylaxis, inform patients of the increased risk for the signs and symptoms of GI bleeding [see Warnings and Precautions (5.2)].

Anaphylactic Reactions

Inform patients of the signs of an anaphylactic reaction (e.g., difficulty breathing, swelling of the face or throat). Instruct patients to seek immediate emergency help if these occur [see Contraindications (4) and Warnings and Precautions (5.5, 5.16)].

Hepatotoxicity

Inform patients of the warning signs and symptoms of hepatotoxicity (e.g., nausea, fatigue, lethargy, diarrhea, pruritus, jaundice, right upper quadrant tenderness, and “flu-like” symptoms). If these occur, instruct patients to stop SYMBRAVO and seek immediate medical therapy [see Warnings and Precautions (5.8)].

Heart Failure and Edema

Advise patients to be alert for the symptoms of congestive heart failure including shortness of breath, unexplained weight gain, or edema and to contact their healthcare provider if such symptoms occur [see Warnings and Precautions (5.10)].

Serious Skin Reactions, including DRESS

Advise patients to stop SYMBRAVO immediately if they develop any type of rash or fever and to contact their healthcare provider as soon as possible [see Contraindications (4), Warnings and Precautions (5.12, 5.13)].

Female Fertility

Advise females of reproductive potential who desire pregnancy that meloxicam, a component of SYMBRAVO, may be associated with a reversible delay in ovulation [see Use in Specific Populations (8.3)].

Lactation

Advise patients to notify their healthcare provider if they are breastfeeding or plan to breastfeed [see Use in Specific Populations (8.2)].

Fetal Toxicity

Inform pregnant women to avoid use of SYMBRAVO and other NSAIDs starting at 30 weeks gestation because of the risk of the premature closing of the fetal ductus arteriosus. If treatment with SYMBRAVO is needed for a pregnant woman between about 20 to 30 weeks gestation, advise her that she may need to be monitored for oligohydramnios, if treatment continues for longer than 48 hours [see Warnings and Precautions (5.14), Use in Specific Populations (8.1)].

Avoid Concomitant Use of NSAIDs

Inform patients that the concomitant use of SYMBRAVO with other NSAIDs or salicylates (e.g., diflunisal, salsalate) is not recommended due to the increased risk of gastrointestinal toxicity, and little or no increase in efficacy [see Warnings and Precautions (5.2), Drug Interactions (7.1)]. Alert patients that NSAIDs may be present in “over the counter” medications for treatment of colds, fever, or insomnia.

Use of NSAIDs and Low-Dose Aspirin

Inform patients not to use low-dose aspirin concomitantly with SYMBRAVO until they talk to their healthcare provider [see Drug Interactions (7.1)].

Medication Overuse Headache

Inform patients that use of acute migraine drugs for 10 or more days per month may lead to an exacerbation of headache, and encourage patients to record headache frequency and drug use (e.g., by keeping a headache diary) [see Warnings and Precautions (5.17)].

Serotonin Syndrome

Patients should be cautioned about the risk of serotonin syndrome with the use of SYMBRAVO, particularly during combined use with SSRIs or SNRIs [see Warnings and Precautions (5.18), Drug Interactions (7.1), Clinical Pharmacology (12.3)].

Ability to Perform Complex Tasks

Since migraines or treatment with SYMBRAVO may cause somnolence and dizziness, instruct patients to evaluate their ability to perform complex tasks during migraine attacks and after administration of SYMBRAVO.

Distributed by:

Axsome Therapeutics, Inc.

New York, NY 10007

AXSOME THERAPEUTICS and SYMBRAVO are trademarks or registered trademarks of Axsome Therapeutics, Inc. in the United States and other countries.

For patent information: www.axsome.com/IP

©2025 Axsome Therapeutics, Inc. All rights reserved.

SYM-USPI-001.001-20250224

MEDICATION GUIDE

SYMBRAVO® (sim-BRAH-voh)

(meloxicam-rizatriptan)

tablets, for oral use

What is the most important information I should know about SYMBRAVO?

SYMBRAVO contains 2 medicines: meloxicam (a nonsteroidal anti-inflammatory drug [NSAID]) and rizatriptan (a triptan).

NSAIDs, including SYMBRAVO, can cause serious side effects, including:

- Increased risk of a heart attack or stroke that can lead to death. This risk may happen early in treatment and may increase:
  - with increasing doses of NSAIDs
  - with longer use of NSAIDs

Do not take SYMBRAVO right before or after a heart surgery called a “coronary artery bypass graft (CABG).”

Avoid taking SYMBRAVO after a recent heart attack unless your healthcare provider tells you to. You may have an increased risk of another heart attack if you take NSAIDs after a recent heart attack.

Stop taking SYMBRAVO and get emergency help right away if you have any of the following symptoms of a heart attack or stroke:

- discomfort in the center of your chest that lasts for more than a few minutes, or that goes away and comes back
- severe tightness, pain, pressure, or heaviness in your chest, throat, neck, or jaw
- pain or discomfort in your arms, back, neck, jaw, or stomach
- shortness of breath with or without chest discomfort
- breaking out in a cold sweat
- nausea or vomiting
- feeling lightheaded
- weakness in one part or on side of your body
- slurred speech

SYMBRAVO is not for people with risk factors for heart disease unless a heart exam is done and shows no problem. You have a higher risk for heart disease if you:

- have high blood pressure
- have high cholesterol levels
- smoke
- are overweight
- have diabetes
- have a family history of diabetes

- Increased risk of bleeding, ulcers, and tears (perforation) of the esophagus (tube leading from the mouth to the stomach), stomach, and intestines:
  - anytime during use
  - without warning symptoms
  - that may cause death

The risk of getting an ulcer or bleeding increases with:

- past history of stomach ulcers, or stomach or intestinal bleeding with use of NSAIDs
- taking medicines called “corticosteroids”, “anticoagulants”, “SSRIs” or “SNRIs” (antidepressants), or aspirin (an antiplatelet)
- increasing doses of NSAIDs
- older age
- longer use of NSAIDs
- poor health
- smoking
- advanced liver disease
- drinking alcohol
- bleeding problems

- SYMBRAVO may cause serious allergic reactions or serious skin reactions that can be life-threatening. Stop taking SYMBRAVO and get emergency help right away if you develop:
  - sudden wheezing
  - swelling of your lips, tongue, throat or body
  - rash
  - fainting
  - problems breathing or swallowing
  - reddening of your skin with blisters or peeling
  - blisters or bleeding of your lips, eye lids, mouth, nose, or genitals

- SYMBRAVO should only be used:
  - exactly as prescribed
  - for the shortest time needed

- SYMBRAVO already contains an NSAID (meloxicam). Do not use SYMBRAVO with other medicines to lessen pain or fever or with other medicines for colds or sleeping problems without talking to your healthcare provider first, because they may contain an NSAID also.

What is SYMBRAVO?

SYMBRAVO is a combination of meloxicam (an NSAID) and rizatriptan (a triptan).

SYMBRAVO is used to treat acute migraine headaches with or without aura in adults.

SYMBRAVO is not for the treatment of other types of migraines such as hemiplegic (that make you unable to move on one side of your body) or basilar (rare form of migraine with aura).

SYMBRAVO is not to be used to prevent or decrease the number of migraine headaches you have.

It is not known if SYMBRAVO is safe and effective for the treatment of cluster headaches.

It is not known if SYMBRAVO is safe and effective in children.

Who should not take SYMBRAVO?

Do not take SYMBRAVO if you:

- have or have had heart problems.
- right before or after heart bypass surgery.
- have or have had a stroke or a transient ischemic attack (TIA).
- have or have had blood vessel problems, including ischemic bowel disease.
- have or had hemiplegic migraines or basilar migraines.
- narrowing of blood vessels of your legs and arms (peripheral vascular disease), stomach (ischemic bowel disease), or kidneys.
- have uncontrolled high blood pressure.
- take a propranolol containing medicines.
- have taken any medicines in the last 24 hours that are called 5-HT1 agonists (triptans) or contain ergotamine.
- take an antidepressant medicine called monoamine oxidase (MAO) inhibitor or have taken a MAO inhibitor within the last 2 weeks.
- are allergic to meloxicam, rizatriptan, NSAIDs or any of the ingredients in SYMBRAVO. See the end of this Medication Guide for a complete list of ingredients in SYMBRAVO.
- have had an asthma attack, hives, or other allergic reaction after taking with aspirin or any other NSAIDs.
- have moderate to severe kidney problems and are at risk of kidney failure or if you are on dialysis.

Talk to your healthcare provider before taking this medicine if you have any of the conditions listed above or if you are not sure if you take any of these medicines.

What should I tell my healthcare provider before taking SYMBRAVO?

Before you take SYMBRAVO, tell your healthcare provider about all of your medical conditions, including if you:

- have or have had heart problems, high blood pressure, chest pain, or shortness of breath.
- have any risk factors for heart problems or blood vessel problems such as:

- high blood pressure
- high cholesterol
- smoking
- obesity

- diabetes
- family history of heart problems
- you are post-menopausal
- you are a male over 40

- have kidney or liver problems.
- have asthma.
- have any other medical condition.
- are pregnant or plan to become pregnant. Taking NSAIDs, including SYMBRAVO, at about 20 weeks of pregnancy or later may harm your unborn baby. If you need to take NSAIDs for more than 2 days when you are between 20 and 30 weeks of pregnancy, your healthcare provider may need to monitor the amount of fluid in your womb around your baby. You should not take NSAIDs after about 30 weeks of pregnancy.
- are breastfeeding or plan to breastfeed. Talk to your healthcare provider about the best way to feed your baby if you take SYMBRAVO.

Tell your healthcare provider about all of the medicines you take, including prescription or over the counter medicines, vitamins, or herbal supplements.

SYMBRAVO and other medicines may affect each other causing side effects. SYMBRAVO may affect the way other medicines work, and other medicines may affect how SYMBRAVO works.

Do not start taking any new medicine without talking to your healthcare provider first.

Especially tell your healthcare provider if you take:

- propranolol containing medicines such as Inderal®, Inderal® LA, or Innopran® XL
- medicines used to help your mood, including SSRIs or SNRIs.
- Aspirin
- Any anticoagulant medicines

Ask your healthcare provider or pharmacist for a list of these medicines if you are not sure.
Know the medicines you take. Keep a list of them to show your healthcare provider and pharmacist when you get a new medicine.

How should I take SYMBRAVO?

- Take SYMBRAVO exactly as your healthcare provider tells you to take it.
- It is not known if taking more than 1 dose of SYMBRAVO in 24 hours is safe and effective. Talk to your healthcare provider about what to do if your headache does not go away or comes back.
- Swallow SYMBRAVO tablets whole.
- Do not crush, divide, or chew SYMBRAVO tablets.
- SYMBRAVO can be taken with or without food.
- If you take too much SYMBRAVO, call your healthcare provider or go to the nearest hospital emergency room right away.

What should I avoid while taking SYMBRAVO?

SYMBRAVO may cause dizziness, weakness, or drowsiness. If you have these symptoms, do not drive a car, use machinery, or do anything that needs you to be alert.

What are the possible side effects of SYMBRAVO?

SYMBRAVO can cause serious side effects, including:

See “What is the most important information I should know about SYMBRAVO?

- heartbeats that are too fast or too slow (arrhythmias)
- new or worse high blood pressure
- heart failure
- liver problems including liver failure
- kidney problems including kidney failure
- low red blood cells (anemia)
- life-threatening skin reactions
- asthma attacks in people who have asthma
- Other side effects of NSAIDs, like SYMBRAVO, include: stomach pain, constipation, diarrhea, gas, heartburn, nausea, vomiting, and dizziness.

- Heart attack.Get emergency help right away if you have any of the following symptoms of a heart attack may include:
  - chest discomfort in the center of your chest that lasts for more than a few minutes or that goes away and comes back
  - chest discomfort that feels like uncomfortable pressure, squeezing, fullness or pain
  - pain or discomfort in your arms, back, neck, jaw or stomach
  - shortness of breath with or without chest discomfort
  - breaking out in a cold sweat
  - nausea or vomiting
  - feeling lightheaded
- Stroke.Get emergency help right away if you have any of the symptoms of a stroke may include the following sudden symptoms:
  - numbness or weakness in your face, arm or leg, especially on one side of your body
  - confusion, problems speaking or understanding
  - problems seeing in 1 or both of your eyes
  - problems walking, dizziness, loss of balance or coordination
  - severe headache with no known cause

- Stomach and intestinal problems (gastrointestinal and colonic ischemic events). Get emergency help right away if you have any of the following symptoms of gastrointestinal and colonic ischemic events including:

- sudden or severe stomach pain
- sudden unexplained weight loss
- severe constipation or diarrhea

- severe stomach pain after meals
- severe nausea or vomiting
- bloody diarrhea

- Problems with blood circulation to your legs and feet(peripheral vascular ischemia). Get emergency help right away if you have any of the following symptoms of peripheral vascular ischemia including:
  - cramping and pain in your legs or hips
  - feeling of heaviness or tightness in your leg muscles
  - burning or aching pain in your feet or toes while resting
  - numbness, tingling, or weakness in your legs
  - cold feeling or color changes in 1 or both legs or feet

- Medication overuse headaches. Some people who use too many SYMBRAVO tablets may have worse headaches (medication overuse headache). If your headaches get worse, your healthcare provider may decide to stop your treatment with SYMBRAVO.

- Serotonin syndrome. A condition called serotonin syndrome can happen when Triptan medicines such as SYMBRAVO are taken with certain other medicines called SSRIs or SNRIs. Stop taking SYMBRAVO and get emergency help right away if you have any of the following symptoms of serotonin syndrome:

- mental changes such as seeing things that are not there (hallucinations); agitation, or coma
- fast heartbeat
- changes in your blood pressure

- high body temperature
- tight muscles
- trouble walking

Stop taking SYMBRAVO and call your healthcare provider right away if you get any of the following symptoms:

- nausea
- more tired or weaker than usual
- diarrhea
- itching
- your skin or eyes look yellow
- indigestion or stomach pain
- flu-like symptoms
- vision problems

- vomit blood
- there is blood in your bowel movement of it is black and sticky like tar
- unusual weight gain
- skin rash or blisters with fever
- swelling of the arms, legs, hands, and feet
- tenderness in your right upper side

The most common side effects of SYMBRAVO include:

- dizziness
- feeling tired

These are not all the possible side effects of SYMBRAVO. Tell your healthcare provider if you have any side effect that bothers you or that does not go away.
For more information, ask your healthcare provider or pharmacist.
Call your doctor for medical advice about side effects. You may report side effects to FDA at 1-800-FDA-1088

Other information about NSAIDs:

- Aspirin is an NSAID, but it does not increase the chance of a heart attack. Aspirin can cause bleeding in the brain, stomach, and intestines. Aspirin can also cause ulcers in the stomach and intestines. Do not take aspirin with SYMBRAVO without talking to your healthcare provider first.
- Some NSAIDs are sold without a prescription (over the counter). Talk to your healthcare provider before using over the counter NSAIDs with SYMBRAVO.

General Information about the safe and effective use of SYMBRAVO.

Medicines are sometimes prescribed for purposes other than those listed in a Medication Guide. Do not use SYMBRAVO for a condition for which it was not prescribed. Do not give SYMBRAVO to other people, even if they have the same symptoms that you have. It may harm them.

This Medication Guide summarizes the most important information about SYMBRAVO. If you would like more information, talk to your healthcare provider. You can ask your healthcare provider or pharmacist for information about SYMBRAVO that is written for health professionals. For more information, go to www.SYMBRAVO.com.

How should I store SYMBRAVO?

- Store SYMBRAVO at room temperature between 68°F to 77°F (20°C to 25°C).
- Safely throw away medicine that is out of date or no longer needed.
- Keep SYMBRAVO and all medicines out of the reach of children.

What are the ingredients in SYMBRAVO?

Active ingredients in SYMBRAVO: meloxicam and rizatriptan.

Inactive ingredients in SYMBRAVO: colloidal silicon dioxide, crospovidone, magnesium stearate, microcrystalline cellulose, partially hydrolyzed polyvinyl alcohol, polyethylene glycol, povidone, pregelatinized starch, sodium bicarbonate, sulfobutyl-ether-ß-cyclodextrin sodium, talc, and titanium dioxide.

Distributed by:

Axsome Therapeutics, Inc.,

New York, NY 10007

AXSOME THERAPEUTICS and SYMBRAVO are trademarks owned by Axsome Therapeutics, Inc. in the United States and other countries. The other brands listed are trademarks owned or licensed to their respective owners and are not owned by or licensed to AXSOME Therapeutics, Inc. The makers of these brands are not affiliated with and do not endorse AXSOME Therapeutics, Inc. or its products.

©2025 AXSOME Therapeutics, Inc.

For more information about SYMBRAVO, visit SYMBRAVO.com or call 1-800-484-1672.

This Medication Guide has been approved by the U.S. Food and Drug Administration Issued: 1/2025

SYM-USMG-001.000-20250130

Principal Display Panel - NDC: 81968-020-09 - 9-count Bottle

NDC 81968-020-09

Rx only 9 Tablets For oral use

SYMBRAVO®

(meloxicam and rizatriptan) tablets

20 mg/10 mg

Attention: Dispense with the accompanying Medication Guide to each patient.

Principal Display Panel - NDC: 81968-020-03 - 3-count Physician Sample

Rx Only NDC 81968-020-03

SYMBRAVO®

(meloxicam and rizatriptan) tablets

20 mg/10 mg

Patient Sample

3 Tablets For oral use

Not or Sale.

Dispense with Medication Guide

Principal Display Panel - NDC: 81968-020-02 - 2-count Physician Sample

Rx Only NDC 81968-020-02

SYMBRAVO®

(meloxicam and rizatriptan) tablets

20 mg/10 mg

Patient Sample

2 Tablets For oral use

Not or Sale.

Dispense with Medication Guide